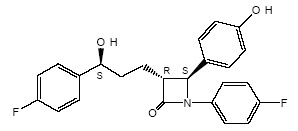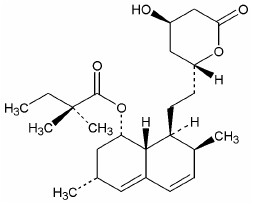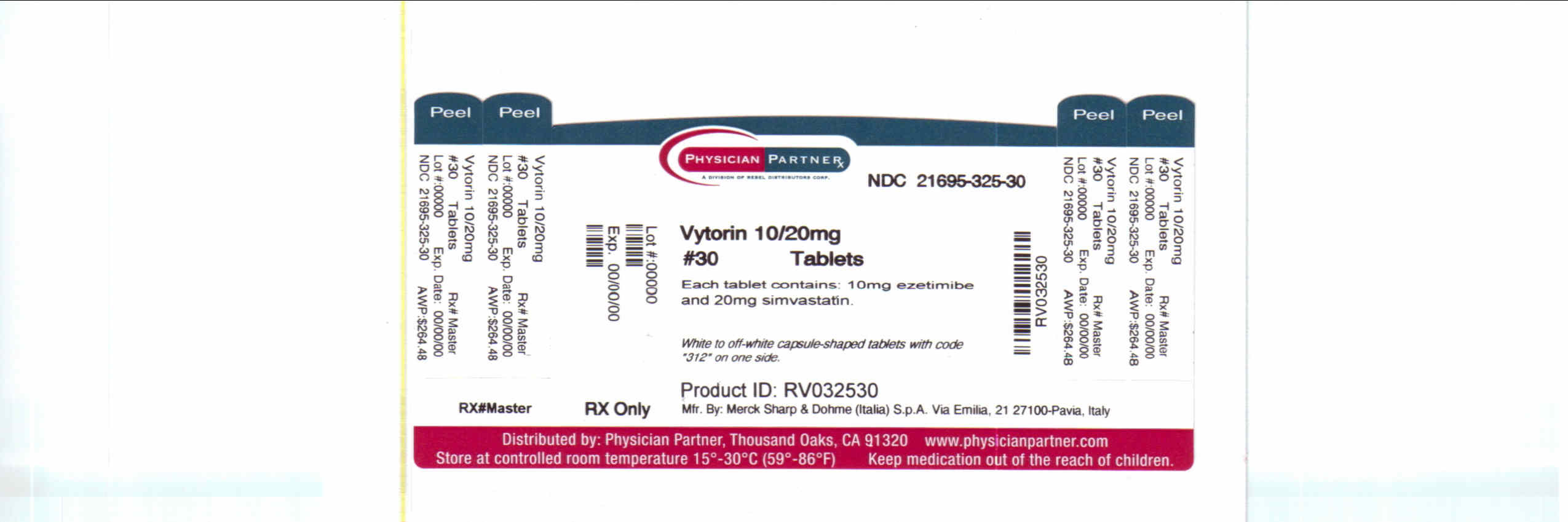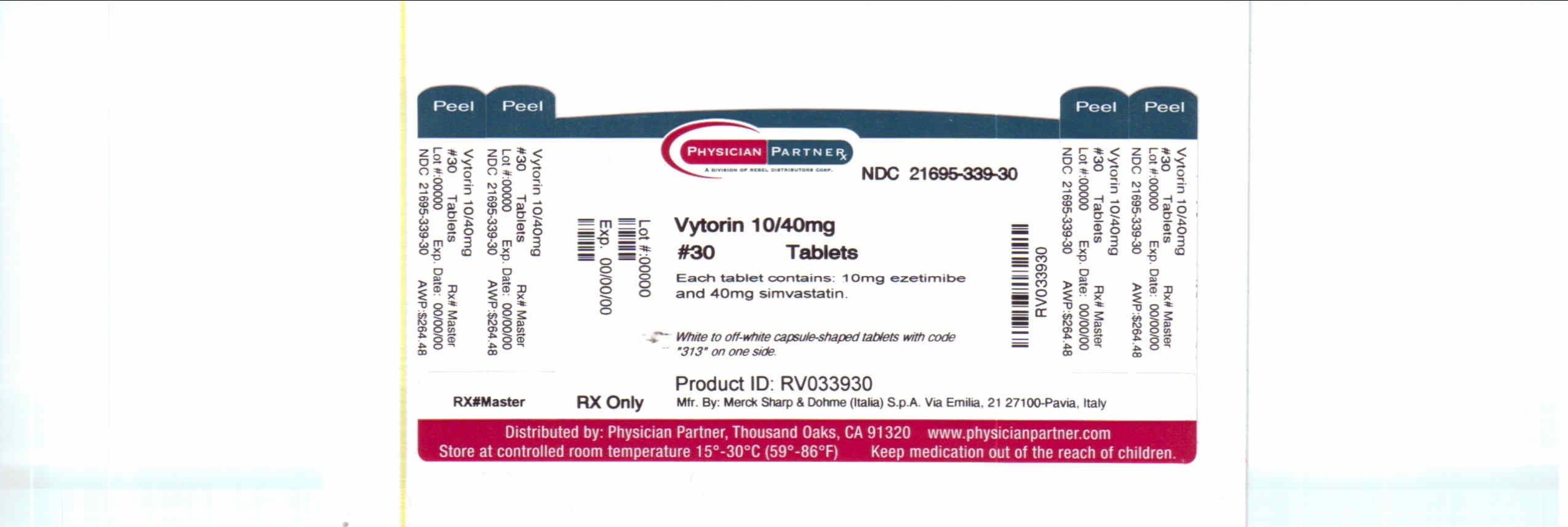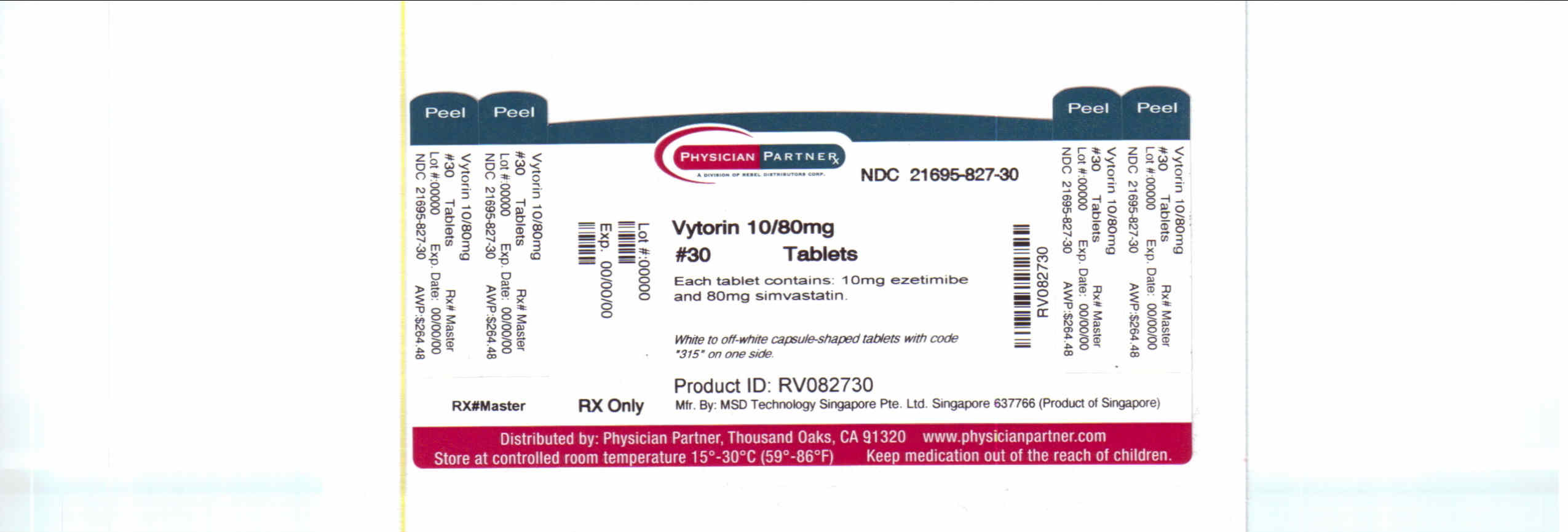 DRUG LABEL: VYTORIN
NDC: 21695-325 | Form: TABLET
Manufacturer: Rebel Distributors Corp
Category: prescription | Type: HUMAN PRESCRIPTION DRUG LABEL
Date: 20101201

ACTIVE INGREDIENTS: ezetimibe 10 mg/1 1; simvastatin 20 mg/1 1
INACTIVE INGREDIENTS: butylated hydroxyanisole; citric acid monohydrate; croscarmellose sodium; HYPROMELLOSES; lactose monohydrate; magnesium stearate; propyl gallate; CELLULOSE, MICROCRYSTALLINE

HIGHLIGHTS OF PRESCRIBING INFORMATION

These highlights do not include all the information needed to use VYTORIN safely and effectively. See full prescribing information for VYTORIN.
VYTORIN (ezetimibe/simvastatin) Tablets
Initial U.S. Approval: 2004

RECENT MAJOR CHANGES

Dosage and Administration

Chinese Patients Taking Lipid-Modifying Doses (≥1 g/day Niacin) of
Niacin-Containing Products (2.6) 03/2010

Coadministration with Other Drugs (2.7) 03/2010

Warnings and Precautions

Myopathy/Rhabdomyolysis (5.1) 03/2010

1 INDICATIONS AND USAGE

VYTORIN®, which contains a cholesterol absorption inhibitor and an HMG-CoA reductase inhibitor (statin), is indicated as adjunctive therapy to diet to:

- reduce elevated total-C, LDL-C, Apo B, TG, and non-HDL-C, and to increase HDL-C in patients with primary (heterozygous familial and non-familial) hyperlipidemia or mixed hyperlipidemia. (1.1)
- reduce elevated total-C and LDL-C in patients with homozygous familial hypercholesterolemia (HoFH), as an adjunct to other lipid-lowering treatments. (1.2)

Limitations of Use (1.3)

- No incremental benefit of VYTORIN on cardiovascular morbidity and mortality over and above that demonstrated for simvastatin has been established. VYTORIN has not been studied in Fredrickson Type I, III, IV, and V dyslipidemias.

2 DOSAGE AND ADMINISTRATION

- Dosage range is 10/10 mg/day through 10/80 mg/day. (2.1)
- Recommended usual starting dose is 10/20 mg/day. (2.1)
- Dosing of VYTORIN should occur either ≥2 hours before or ≥4 hours after administration of a bile acid sequestrant. (2.7, 7.5)

3 DOSAGE FORMS AND STRENGTHS

- Tablets (ezetimibe mg/simvastatin mg): 10/10, 10/20, 10/40, 10/80 (3)

4 CONTRAINDICATIONS

- Hypersensitivity to any component of this medication (4, 6.2)
- Active liver disease or unexplained persistent elevations of hepatic transaminase levels (4, 5.2)
- Women who are pregnant or may become pregnant (4, 8.1)
- Nursing mothers (4, 8.3)

5 WARNINGS AND PRECAUTIONS

- Patients should be advised to report promptly any symptoms of myopathy. VYTORIN should be discontinued immediately if myopathy is diagnosed or suspected. (5.1)
- Skeletal muscle effects (e.g., myopathy and rhabdomyolysis): Risks increase with higher doses and concomitant use of certain CYP3A4 inhibitors, gemfibrozil, cyclosporine, danazol, amiodarone, verapamil, and diltiazem. Predisposing factors include advanced age (≥65), uncontrolled hypothyroidism, and renal impairment. (5.1, 8.5, 8.6)
- Liver enzyme abnormalities and monitoring: Persistent elevations in hepatic transaminase can occur. Monitor liver enzymes before and during treatment. Patients titrated to the 10/80-mg dose should receive additional liver function tests. (5.2)
- VYTORIN is not recommended in patients with moderate or severe hepatic impairment. (5.3, 12.3)

6 ADVERSE REACTIONS

- Common (incidence ≥2% and greater than placebo) adverse reactions in clinical trials: headache, increased ALT, myalgia, upper respiratory tract infection, and diarrhea. (6.1)
  To report SUSPECTED ADVERSE REACTIONS, contact Merck/Schering-Plough Pharmaceuticals at 1-866-637-2501 or FDA at 1-800-FDA-1088 or www.fda.gov/medwatch.

7 DRUG INTERACTIONS

Drug Interactions Associated with Increased Risk of Myopathy/Rhabdomyolysis (2.7, 5.1, 7.1, 7.2, 7.3, 7.6, 7.8)
Interacting Agents | Prescribing Recommendations
Itraconazole, ketoconazole, erythromycin, clarithromycin, telithromycin, HIV protease inhibitors, nefazodone, fibrates | Avoid VYTORIN
Cyclosporine, danazol | Do not exceed 10/10 mg VYTORIN daily
Amiodarone, verapamil | Do not exceed 10/20 mg VYTORIN daily
Diltiazem | Do not exceed 10/40 mg VYTORIN daily
Grapefruit juice | Avoid large quantities of grapefruit juice (>1 quart daily)

- Cyclosporine: Combination increases exposure of ezetimibe and cyclosporine. Cyclosporine concentrations should be monitored. (7.6, 12.3)
- Coumarin anticoagulants: simvastatin prolongs INR. Achieve stable INR prior to starting VYTORIN. Monitor INR frequently until stable upon initiation or alteration of VYTORIN therapy. (7.9)
- Cholestyramine: Combination decreases exposure of ezetimibe. (2.7, 7.5)

8 USE IN SPECIFIC POPULATIONS

- Severe renal impairment: Caution should be exercised and the patient should be closely monitored. (2.4, 8.6)

FULL PRESCRIBING INFORMATION

1 INDICATIONS AND USAGE

Therapy with lipid-altering agents should be only one component of multiple risk factor intervention in individuals at significantly increased risk for atherosclerotic vascular disease due to hypercholesterolemia. Drug therapy is indicated as an adjunct to diet when the response to a diet restricted in saturated fat and cholesterol and other nonpharmacologic measures alone has been inadequate.

1.1 Primary Hyperlipidemia

VYTORIN is indicated for the reduction of elevated total cholesterol (total-C), low-density lipoprotein cholesterol (LDL-C), apolipoprotein B (Apo B), triglycerides (TG), and non-high-density lipoprotein cholesterol (non-HDL-C), and to increase high-density lipoprotein cholesterol (HDL-C) in patients with primary (heterozygous familial and non-familial) hyperlipidemia or mixed hyperlipidemia.

1.2 Homozygous Familial Hypercholesterolemia (HoFH)

VYTORIN is indicated for the reduction of elevated total-C and LDL-C in patients with homozygous familial hypercholesterolemia, as an adjunct to other lipid-lowering treatments (e.g., LDL apheresis) or if such treatments are unavailable.

1.3 Limitations of Use

No incremental benefit of VYTORIN on cardiovascular morbidity and mortality over and above that demonstrated for simvastatin has been established. VYTORIN has not been studied in Fredrickson type I, III, IV, and V dyslipidemias.

2 DOSAGE AND ADMINISTRATION

2.1 Recommended Dosing

The dosage range is 10/10 mg/day through 10/80 mg/day. The recommended usual starting dose is 10/20 mg/day. VYTORIN should be taken as a single daily dose in the evening, with or without food. Initiation of therapy with 10/10 mg/day may be considered for patients requiring less aggressive LDL-C reductions. Patients who require a larger reduction in LDL-C (greater than 55%) may be started at 10/40 mg/day. After initiation or titration of VYTORIN, lipid levels may be analyzed after 2 or more weeks and dosage adjusted, if needed.

2.2 Patients with Homozygous Familial Hypercholesterolemia

The recommended dosage for patients with homozygous familial hypercholesterolemia is VYTORIN 10/40 mg/day or 10/80 mg/day in the evening. VYTORIN should be used as an adjunct to other lipid-lowering treatments (e.g., LDL apheresis) in these patients or if such treatments are unavailable.

2.3 Patients with Hepatic Impairment

No dosage adjustment is necessary in patients with mild hepatic impairment [see Warnings and Precautions (5.3)].

2.4 Patients with Renal Impairment

No dosage adjustment is necessary in patients with mild or moderate renal impairment. However, for patients with severe renal insufficiency, VYTORIN should not be started unless the patient has already tolerated treatment with simvastatin at a dose of 5 mg or higher. Caution should be exercised when VYTORIN is administered to these patients, and they should be closely monitored [see Warnings and Precautions (5.1); Clinical Pharmacology (12.3)].

2.5 Geriatric Patients

No dosage adjustment is necessary in geriatric patients [see Clinical Pharmacology (12.3)].

2.6 Chinese Patients Taking Lipid-Modifying Doses (≥1 g/day Niacin) of Niacin-Containing Products

Because of an increased risk for myopathy, caution should be used when treating Chinese patients with VYTORIN coadministered with lipid-modifying doses (≥1 g/day niacin) of niacin-containing products. Because the risk for myopathy is dose-related, Chinese patients should not receive VYTORIN 10/80 mg coadministered with lipid-modifying doses of niacin-containing products. The cause of the increased risk of myopathy is not known. It is also unknown if the risk for myopathy with coadministration of simvastatin with lipid-modifying doses of niacin-containing products observed in Chinese patients applies to other Asian patients. [See Warnings and Precautions (5.1).]

2.7 Coadministration with Other Drugs

[See Warnings and Precautions (5.1) and Drug Interactions (7).]

Bile Acid Sequestrants

Dosing of VYTORIN should occur either ≥2 hours before or ≥4 hours after administration of a bile acid sequestrant [see Drug Interactions (7.5)].

Cyclosporine or Danazol

Caution should be exercised when initiating VYTORIN in the setting of cyclosporine. In patients taking cyclosporine or danazol, VYTORIN should not be started unless the patient has already tolerated treatment with simvastatin at a dose of 5 mg or higher. The dose of VYTORIN should not exceed 10/10 mg/day [see Drug Interactions (7.6)].

Amiodarone or Verapamil

In patients taking amiodarone or verapamil concomitantly with VYTORIN, the dose should not exceed 10/20 mg/day [see Warnings and Precautions (5.1) and Drug Interactions (7.3)].

Diltiazem

The dose of VYTORIN should not exceed 10/40 mg/day [see Warnings and Precautions (5.1), Drug Interactions (7.3), and Clinical Pharmacology (12.3)].

Other Concomitant Lipid-Lowering Therapy

The safety and effectiveness of VYTORIN administered with fibrates have not been established. Therefore, the combination of VYTORIN and fibrates should be avoided [see Warnings and Precautions (5.1) and Drug Interactions (7.2 and 7.8)].

There is an increased risk of myopathy when simvastatin is used concomitantly with fibrates (especially gemfibrozil). Combination therapy with gemfibrozil should be avoided because of an increase in simvastatin exposure with concomitant use. [See Warnings and Precautions (5.1) and Drug Interactions (7.2 and 7.8).]

3 DOSAGE FORMS AND STRENGTHS

- VYTORIN® 10/10, (ezetimibe 10 mg/simvastatin 10 mg tablets) are white to off-white capsule-shaped tablets with code “311” on one side.
- VYTORIN® 10/20, (ezetimibe 10 mg/simvastatin 20 mg tablets) are white to off-white capsule-shaped tablets with code “312” on one side.
- VYTORIN® 10/40, (ezetimibe 10 mg/simvastatin 40 mg tablets) are white to off-white capsule-shaped tablets with code “313” on one side.
- VYTORIN® 10/80, (ezetimibe 10 mg/simvastatin 80 mg tablets) are white to off-white capsule-shaped tablets with code “315” on one side.

4 CONTRAINDICATIONS

Hypersensitivity to any component of this medication [see Adverse Reactions (6.2)].

Active liver disease or unexplained persistent elevations in hepatic transaminase levels [see Warnings and Precautions (5.2)].

Women who are pregnant or may become pregnant. Serum cholesterol and triglycerides increase during normal pregnancy, and cholesterol or cholesterol derivatives are essential for fetal development. Because HMG-CoA reductase inhibitors (statins), such as simvastatin, decrease cholesterol synthesis and possibly the synthesis of other biologically active substances derived from cholesterol, VYTORIN may cause fetal harm when administered to a pregnant woman. Atherosclerosis is a chronic process and the discontinuation of lipid-lowering drugs during pregnancy should have little impact on the outcome of long-term therapy of primary hypercholesterolemia. There are no adequate and well-controlled studies of VYTORIN use during pregnancy; however, in rare reports congenital anomalies were observed following intrauterine exposure to statins. In rat and rabbit animal reproduction studies, simvastatin revealed no evidence of teratogenicity. VYTORIN should be administered to women of childbearing age only when such patients are highly unlikely to conceive. If the patient becomes pregnant while taking this drug, VYTORIN should be discontinued immediately and the patient should be apprised of the potential hazard to the fetus [see Use in Specific Populations (8.1)].

Nursing mothers. It is not known whether simvastatin is excreted into human milk; however, a small amount of another drug in this class does pass into breast milk. Because statins have the potential for serious adverse reactions in nursing infants, women who require VYTORIN treatment should not breast-feed their infants [see Use in Specific Populations (8.3)].

5 WARNINGS AND PRECAUTIONS

5.1 Myopathy/Rhabdomyolysis

In clinical trials, there was no excess of myopathy or rhabdomyolysis associated with ezetimibe compared with the relevant control arm (placebo or statin alone). However, myopathy and rhabdomyolysis are known adverse reactions to statins and other lipid-lowering drugs. In clinical trials, the incidence of CK >10 X the upper limit of normal (ULN) was 0.2% for VYTORIN, 0.6% for placebo, 0.0% for ezetimibe, and 0.3% for all simvastatin doses.

Simvastatin, like other statins, occasionally causes myopathy manifested as muscle pain, tenderness or weakness with creatine kinase above 10 X ULN. Myopathy sometimes takes the form of rhabdomyolysis with or without acute renal failure secondary to myoglobinuria, and rare fatalities have occurred. The risk of myopathy is increased by high levels of statin activity in plasma. Predisposing factors for myopathy include advanced age (≥65 years), uncontrolled hypothyroidism, and renal impairment.

As with other statins, the risk of myopathy/rhabdomyolysis is dose related. In a clinical trial database in which 41,050 patients were treated with simvastatin with 24,747 (approximately 60%) treated for at least 4 years, the incidence of myopathy was approximately 0.02%, 0.08% and 0.53% at 20, 40 and 80 mg/day, respectively. In these trials, patients were carefully monitored and some interacting medicinal products were excluded.

In post-marketing experience with ezetimibe, cases of myopathy and rhabdomyolysis have been reported. Most patients who developed rhabdomyolysis were taking a statin prior to initiating ezetimibe. However, rhabdomyolysis has been reported very rarely with ezetimibe monotherapy and very rarely with the addition of ezetimibe to agents known to be associated with increased risk of rhabdomyolysis, such as fibrates.

All patients starting therapy with VYTORIN or whose dose of VYTORIN is being increased should be advised of the risk of myopathy and told to report promptly any unexplained muscle pain, tenderness or weakness. VYTORIN therapy should be discontinued immediately if myopathy is diagnosed or suspected. In most cases, muscle symptoms and CK increases resolved when simvastatin treatment was promptly discontinued. Periodic CK determinations may be considered in patients starting therapy with simvastatin or whose dose is being increased, but there is no assurance that such monitoring will prevent myopathy.

Many of the patients who have developed rhabdomyolysis on therapy with simvastatin have had complicated medical histories, including renal insufficiency usually as a consequence of long-standing diabetes mellitus. Such patients taking VYTORIN merit closer monitoring. Therapy with VYTORIN should be temporarily stopped a few days prior to elective major surgery and when any major medical or surgical condition supervenes.

Drug Interactions

The risk of myopathy and rhabdomyolysis is increased by high levels of statin activity in plasma. Simvastatin is metabolized by the cytochrome P450 isoform 3A4. Certain drugs that inhibit this metabolic pathway can raise the plasma levels of simvastatin and may increase the risk of myopathy. These include itraconazole, ketoconazole, and other antifungal azoles, the macrolide antibiotics erythromycin and clarithromycin, and the ketolide antibiotic telithromycin, HIV protease inhibitors, the antidepressant nefazodone, or large quantities of grapefruit juice (>1 quart daily). The use of VYTORIN concomitantly with these CYP3A4 inhibitors should be avoided. If treatment with itraconazole, ketoconazole, erythromycin, clarithromycin or telithromycin is unavoidable, therapy with VYTORIN should be suspended during the course of treatment. [See Drug Interactions (7).]

The benefits of the combined use of VYTORIN with the following drugs should be carefully weighed against the potential risks of combinations: gemfibrozil, other lipid-lowering drugs (other fibrates or ≥1 g/day of niacin), cyclosporine, danazol, amiodarone, verapamil, or diltiazem.

Caution should be used when prescribing other fibrates with VYTORIN, as these agents can cause myopathy when given alone.

Cases of myopathy/rhabdomyolysis have been observed with simvastatin coadministered with lipid-modifying doses (≥1 g/day niacin) of niacin-containing products. In an ongoing, double-blind, randomized cardiovascular outcomes trial, an independent safety monitoring committee identified that the incidence of myopathy is higher in Chinese compared with non-Chinese patients taking simvastatin 40 mg or ezetimibe/simvastatin 10/40 mg coadministered with lipid-modifying doses of a niacin-containing product. Because the risk for myopathy is dose-related, Chinese patients should not receive VYTORIN 10/80 mg coadministered with lipid-modifying doses of niacin-containing products. It is unknown if the risk for myopathy with coadministration of simvastatin with lipid-modifying doses of niacin-containing products observed in Chinese patients applies to other Asian patients.

Prescribing recommendations for interacting agents are summarized in Table 1 [see also Dosage and Administration (2.7), Drug Interactions (7), and Clinical Pharmacology (12.3)].

Table 1: Drug Interactions Associated with Increased Risk of Myopathy/Rhabdomyolysis
Interacting Agents | Prescribing Recommendations
Itraconazole Ketoconazole Erythromycin Clarithromycin Telithromycin HIV protease inhibitors Nefazodone Fibrates [Combination therapy with fibrates should be avoided; however, although not recommended, if VYTORIN is used in combination with gemfibrozil, the dose should not exceed 10/10 mg daily.] | Avoid VYTORIN
Cyclosporine [The benefits of the use of VYTORIN in patients receiving cyclosporine or danazol should be carefully weighed against the risks of these combinations.] Danazol | Do not exceed 10/10 mg VYTORIN daily
Amiodarone [The combined use of VYTORIN at doses higher than 10/20 mg daily with amiodarone or verapamil should be avoided unless the clinical benefit is likely to outweigh the increased risk of myopathy.] Verapamil | Do not exceed 10/20 mg VYTORIN daily
Diltiazem [The combined use of VYTORIN at doses higher than 10/40 mg daily with diltiazem should be avoided unless the clinical benefit is likely to outweigh the increased risk of myopathy.] | Do not exceed 10/40 mg VYTORIN daily
Grapefruit juice | Avoid large quantities of grapefruit juice (>1 quart daily)

5.2 Liver Enzymes

In three placebo-controlled, 12-week trials, the incidence of consecutive elevations (≥3 X ULN) in serum transaminases was 1.7% overall for patients treated with VYTORIN and appeared to be dose-related with an incidence of 2.6% for patients treated with VYTORIN 10/80. In controlled long-term (48-week) extensions, which included both newly-treated and previously-treated patients, the incidence of consecutive elevations (≥3 X ULN) in serum transaminases was 1.8% overall and 3.6% for patients treated with VYTORIN 10/80. These elevations in transaminases were generally asymptomatic, not associated with cholestasis, and returned to baseline after discontinuation of therapy or with continued treatment.

It is recommended that liver function tests be performed before the initiation of treatment with VYTORIN, and thereafter when clinically indicated. Patients titrated to the 10/80-mg dose should receive an additional test prior to titration, 3 months after titration to the 10/80-mg dose, and periodically thereafter (e.g., semiannually) for the first year of treatment. Patients who develop increased transaminase levels should be monitored with a second liver function evaluation to confirm the finding and be followed thereafter with frequent liver function tests until the abnormality(ies) return to normal. Should an increase in AST or ALT of 3 X ULN or greater persist, withdrawal of therapy with VYTORIN is recommended.

VYTORIN should be used with caution in patients who consume substantial quantities of alcohol and/or have a past history of liver disease. Active liver diseases or unexplained persistent transaminase elevations are contraindications to the use of VYTORIN.

5.3 Hepatic Impairment

Due to the unknown effects of the increased exposure to ezetimibe in patients with moderate or severe hepatic impairment, VYTORIN is not recommended in these patients. [See Clinical Pharmacology (12.3).]

6 ADVERSE REACTIONS

The following serious adverse reactions are discussed in greater detail in other sections of the label:

- Rhabdomyolysis and myopathy [see Warnings and Precautions (5.1)]
- Liver enzyme abnormalities [see Warnings and Precautions (5.2)]

6.1 Clinical Trials Experience

VYTORIN

Because clinical studies are conducted under widely varying conditions, adverse reaction rates observed in the clinical studies of a drug cannot be directly compared to rates in the clinical studies of another drug and may not reflect the rates observed in practice.

In the VYTORIN (ezetimibe/simvastatin) placebo-controlled clinical trials database of 1420 patients (age range 20-83 years, 52% women, 87% Caucasians, 3% Blacks, 5% Hispanics, 3% Asians) with a median treatment duration of 27 weeks, 5% of patients on VYTORIN and 2.2% of patients on placebo discontinued due to adverse reactions.

The most common adverse reactions in the group treated with VYTORIN that led to treatment discontinuation and occurred at a rate greater than placebo were:

- Increased ALT (0.9%)
- Myalgia (0.6%)
- Increased AST (0.4%)
- Back pain (0.4%)

The most commonly reported adverse reactions (incidence ≥2% and greater than placebo) in controlled clinical trials were: headache (5.8%), increased ALT (3.7%), myalgia (3.6%), upper respiratory tract infection (3.6%), and diarrhea (2.8%).

VYTORIN has been evaluated for safety in more than 10,189 patients in clinical trials.

Table 2 summarizes the frequency of clinical adverse reactions reported in ≥2% of patients treated with VYTORIN (n=1420) and at an incidence greater than placebo, regardless of causality assessment, from four placebo-controlled trials.

Table 2 [Includes two placebo-controlled combination studies in which the active ingredients equivalent to VYTORIN were coadministered and two placebo-controlled studies in which VYTORIN was administered.] : Clinical Adverse Reactions Occurring in ≥2% of Patients Treated with VYTORIN and at an Incidence Greater than Placebo, Regardless of Causality
Body System/Organ Class Adverse Reaction | Placebo (%) n=371 | Ezetimibe 10 mg (%) n=302 | Simvastatin [All doses.] (%) n=1234 | VYTORIN (%) n=1420
Body as a whole – general disorders
Headache | 5.4 | 6.0 | 5.9 | 5.8
Gastrointestinal system disorders
Diarrhea | 2.2 | 5.0 | 3.7 | 2.8
Infections and infestations
Influenza | 0.8 | 1.0 | 1.9 | 2.3
Upper respiratory tract infection | 2.7 | 5.0 | 5.0 | 3.6
Musculoskeletal and connective tissue disorders
Myalgia | 2.4 | 2.3 | 2.6 | 3.6
Pain in extremity | 1.3 | 3.0 | 2.0 | 2.3

Ezetimibe

Other adverse reactions reported with ezetimibe in placebo-controlled studies, regardless of causality assessment: Musculoskeletal system disorders: arthralgia; Infections and infestations: sinusitis; Body as a whole – general disorders: fatigue.

Simvastatin

Other adverse reactions reported with simvastatin in placebo-controlled clinical studies, regardless of causality assessment: Cardiac disorders: atrial fibrillation; Ear and labyrinth disorders: vertigo; Gastrointestinal disorders: abdominal pain, constipation, dyspepsia, flatulence, gastritis; Skin and subcutaneous tissue disorders: eczema, rash; Endocrine disorders: diabetes mellitus; Infections and infestations: bronchitis, sinusitis, urinary tract infections; Body as a whole – general disorders: asthenia, edema/swelling; Psychiatric disorders: insomnia.

Laboratory Tests

Marked persistent increases of hepatic serum transaminases have been noted [see Warnings and Precautions (5.2)]. Elevated alkaline phosphatase and γ-glutamyl transpeptidase have been reported. About 5% of patients taking simvastatin had elevations of CK levels of 3 or more times the normal value on one or more occasions. This was attributable to the noncardiac fraction of CK [see Warnings and Precautions (5.1)].

6.2 Post-Marketing Experience

Because the below reactions are reported voluntarily from a population of uncertain size, it is generally not possible to reliably estimate their frequency or establish a causal relationship to drug exposure.

The following adverse reactions have been reported in post-marketing experience for VYTORIN or ezetimibe or simvastatin: pruritus; alopecia; erythema multiforme; a variety of skin changes (e.g., nodules, discoloration, dryness of skin/mucous membranes, changes to hair/nails); dizziness; muscle cramps; myalgia; arthralgia; pancreatitis; memory impairment; paresthesia; peripheral neuropathy; vomiting; nausea; anemia; erectile dysfunction; interstitial lung disease; myopathy/rhabdomyolysis [see Warnings and Precautions (5.1)]; hepatitis/jaundice; hepatic failure; depression; cholelithiasis; cholecystitis; thrombocytopenia; elevations in liver transaminases; elevated creatine phosphokinase.

Hypersensitivity reactions, including anaphylaxis, angioedema, rash, and urticaria have been reported.

In addition, an apparent hypersensitivity syndrome has been reported rarely that has included one or more of the following features: anaphylaxis, angioedema, lupus erythematous-like syndrome, polymyalgia rheumatica, dermatomyositis, vasculitis, purpura, thrombocytopenia, leukopenia, hemolytic anemia, positive ANA, ESR increase, eosinophilia, arthritis, arthralgia, urticaria, asthenia, photosensitivity, fever, chills, flushing, malaise, dyspnea, toxic epidermal necrolysis, erythema multiforme, including Stevens-Johnson syndrome.

7 DRUG INTERACTIONS

[See Clinical Pharmacology (12.3).]

VYTORIN

7.1 CYP3A4 Interactions

The risk of myopathy is increased by reducing the elimination of the simvastatin component of VYTORIN. Hence when VYTORIN is used with an inhibitor of CYP3A4 (e.g., as listed below), elevated plasma levels of HMG-CoA reductase inhibitory activity can increase the risk of myopathy and rhabdomyolysis, particularly with higher doses of VYTORIN. [See Warnings and Precautions (5.1) and Clinical Pharmacology (12.3).]

Itraconazole, ketoconazole, and other antifungal azoles

Macrolide antibiotics erythromycin, clarithromycin, and the ketolide antibiotic telithromycin

HIV protease inhibitors

Antidepressant nefazodone

Grapefruit juice in large quantities (>1 quart daily)

Concomitant use of these drugs and any medication labeled as having a strong inhibitory effect on CYP3A4 should be avoided unless the benefits of combined therapy outweigh the increased risk. If treatment with itraconazole, ketoconazole, erythromycin, clarithromycin or telithromycin is unavoidable, therapy with VYTORIN should be suspended during the course of treatment.

7.2 Lipid-Lowering Drugs That Can Cause Myopathy When Given Alone

The risk of myopathy is increased by gemfibrozil and to a lesser extent by other fibrates [see Warnings and Precautions (5.1)].

7.3 Amiodarone, Verapamil, or Diltiazem

The risk of myopathy/rhabdomyolysis is increased by concomitant administration of amiodarone, verapamil, or diltiazem with higher doses of VYTORIN [see Warnings and Precautions (5.1)].

7.4 Niacin

Cases of myopathy/rhabdomyolysis have been observed with simvastatin coadministered with lipid-modifying doses (≥1 g/day niacin) of niacin-containing products. In particular, caution should be used when treating Chinese patients with VYTORIN coadministered with lipid-modifying doses of niacin-containing products. Because the risk for myopathy is dose-related, Chinese patients should not receive VYTORIN 10/80 mg coadministered with lipid-modifying doses of niacin-containing products. [See Warnings and Precautions (5.1).]

7.5 Cholestyramine

Concomitant cholestyramine administration decreased the mean AUC of total ezetimibe approximately 55%. The incremental LDL-C reduction due to adding VYTORIN to cholestyramine may be reduced by this interaction.

7.6 Cyclosporine or Danazol

The risk of myopathy/rhabdomyolysis is increased by concomitant administration of cyclosporine or danazol particularly with higher doses of VYTORIN [see Warnings and Precautions (5.1) and Clinical Pharmacology (12.3)].

Caution should be exercised when using VYTORIN and cyclosporine concomitantly due to increased exposure to both ezetimibe and cyclosporine [see Dosage and Administration (2.7)]. Cyclosporine concentrations should be monitored in patients receiving VYTORIN and cyclosporine [see Clinical Pharmacology (12.3)].

The degree of increase in ezetimibe exposure may be greater in patients with severe renal impairment. In patients treated with cyclosporine, the potential effects of the increased exposure to ezetimibe from concomitant use should be carefully weighed against the benefits of alterations in lipid levels provided by ezetimibe. [See Warnings and Precautions (5.1) and Clinical Pharmacology (12.3).]

7.7 Digoxin

In one study, concomitant administration of digoxin with simvastatin resulted in a slight elevation in plasma digoxin concentrations. Patients taking digoxin should be monitored appropriately when VYTORIN is initiated.

7.8 Fibrates

The safety and effectiveness of VYTORIN administered with fibrates have not been established.

Fibrates may increase cholesterol excretion into the bile, leading to cholelithiasis. In a preclinical study in dogs, ezetimibe increased cholesterol in the gallbladder bile [see Animal Toxicology and/or Pharmacology (13.2)]. Coadministration of VYTORIN with fibrates is not recommended until use in patients is studied. [See Warnings and Precautions (5.1).]

7.9 Coumarin Anticoagulants

Simvastatin 20-40 mg/day modestly potentiated the effect of coumarin anticoagulants: the prothrombin time, reported as International Normalized Ratio (INR), increased from a baseline of 1.7 to 1.8 and from 2.6 to 3.4 in a normal volunteer study and in a hypercholesterolemic patient study, respectively. With other statins, clinically evident bleeding and/or increased prothrombin time has been reported in a few patients taking coumarin anticoagulants concomitantly. In such patients, prothrombin time should be determined before starting VYTORIN and frequently enough during early therapy to ensure that no significant alteration of prothrombin time occurs. Once a stable prothrombin time has been documented, prothrombin times can be monitored at the intervals usually recommended for patients on coumarin anticoagulants. If the dose of VYTORIN is changed or discontinued, the same procedure should be repeated. Simvastatin therapy has not been associated with bleeding or with changes in prothrombin time in patients not taking anticoagulants.

Concomitant administration of ezetimibe (10 mg once daily) had no significant effect on bioavailability of warfarin and prothrombin time in a study of twelve healthy adult males. There have been post-marketing reports of increased INR in patients who had ezetimibe added to warfarin. Most of these patients were also on other medications.

The effect of VYTORIN on the prothrombin time has not been studied.

8 USE IN SPECIFIC POPULATIONS

8.1 Pregnancy

Pregnancy Category X.

[See Contraindications (4).]

VYTORIN

VYTORIN is contraindicated in women who are or may become pregnant. Lipid-lowering drugs offer no benefit during pregnancy, because cholesterol and cholesterol derivatives are needed for normal fetal development. Atherosclerosis is a chronic process, and discontinuation of lipid-lowering drugs during pregnancy should have little impact on long-term outcomes of primary hypercholesterolemia therapy. There are no adequate and well-controlled studies of VYTORIN use during pregnancy; however, there are rare reports of congenital anomalies in infants exposed to statins in utero. Animal reproduction studies of simvastatin in rats and rabbits showed no evidence of teratogenicity. Serum cholesterol and triglycerides increase during normal pregnancy, and cholesterol or cholesterol derivatives are essential for fetal development. Because statins, such as simvastatin, decrease cholesterol synthesis and possibly the synthesis of other biologically active substances derived from cholesterol, VYTORIN may cause fetal harm when administered to a pregnant woman. If VYTORIN is used during pregnancy or if the patient becomes pregnant while taking this drug, the patient should be apprised of the potential hazard to the fetus.

Women of childbearing potential, who require VYTORIN treatment for a lipid disorder, should be advised to use effective contraception. For women trying to conceive, discontinuation of VYTORIN should be considered. If pregnancy occurs, VYTORIN should be immediately discontinued.

Ezetimibe

In oral (gavage) embryo-fetal development studies of ezetimibe conducted in rats and rabbits during organogenesis, there was no evidence of embryolethal effects at the doses tested (250, 500, 1000 mg/kg/day). In rats, increased incidences of common fetal skeletal findings (extra pair of thoracic ribs, unossified cervical vertebral centra, shortened ribs) were observed at 1000 mg/kg/day (~10 times the human exposure at 10 mg daily based on AUC0-24hr for total ezetimibe). In rabbits treated with ezetimibe, an increased incidence of extra thoracic ribs was observed at 1000 mg/kg/day (150 times the human exposure at 10 mg daily based on AUC0-24hr for total ezetimibe). Ezetimibe crossed the placenta when pregnant rats and rabbits were given multiple oral doses.

Multiple-dose studies of ezetimibe coadministered with statins in rats and rabbits during organogenesis result in higher ezetimibe and statin exposures. Reproductive findings occur at lower doses in coadministration therapy compared to monotherapy.

Simvastatin

Simvastatin was not teratogenic in rats or rabbits at doses (25, 10 mg/kg/day, respectively) that resulted in 3 times the human exposure based on mg/m^2 surface area. However, in studies with another structurally-related statin, skeletal malformations were observed in rats and mice.

There are rare reports of congenital anomalies following intrauterine exposure to statins. In a review [Manson, J.M., Freyssinges, C., Ducrocq, M.B., Stephenson, W.P., Postmarketing Surveillance of Lovastatin and Simvastatin Exposure During Pregnancy, Reproductive Toxicology, 10(6):439-446, 1996.] of approximately 100 prospectively followed pregnancies in women exposed to simvastatin or another structurally-related statin, the incidences of congenital anomalies, spontaneous abortions and fetal deaths/stillbirths did not exceed what would be expected in the general population. The number of cases is adequate only to exclude a 3- to 4-fold increase in congenital anomalies over the background incidence. In 89% of the prospectively followed pregnancies, drug treatment was initiated prior to pregnancy and was discontinued at some point in the first trimester when pregnancy was identified.

8.3 Nursing Mothers

It is not known whether simvastatin is excreted in human milk. Because a small amount of another drug in this class is excreted in human milk and because of the potential for serious adverse reactions in nursing infants, women taking simvastatin should not nurse their infants. A decision should be made whether to discontinue nursing or discontinue drug, taking into account the importance of the drug to the mother [see Contraindications (4)].

In rat studies, exposure to ezetimibe in nursing pups was up to half of that observed in maternal plasma. It is not known whether ezetimibe or simvastatin are excreted into human breast milk. Because a small amount of another drug in the same class as simvastatin is excreted in human milk and because of the potential for serious adverse reactions in nursing infants, women who are nursing should not take VYTORIN [see Contraindications (4)].

8.4 Pediatric Use

The effects of ezetimibe coadministered with simvastatin (n=126) compared to simvastatin monotherapy (n=122) have been evaluated in adolescent boys and girls with heterozygous familial hypercholesterolemia (HeFH). In a multicenter, double-blind, controlled study followed by an open-label phase, 142 boys and 106 postmenarchal girls, 10 to 17 years of age (mean age 14.2 years, 43% females, 82% Caucasians, 4% Asian, 2% Blacks, 13% multi-racial) with HeFH were randomized to receive either ezetimibe coadministered with simvastatin or simvastatin monotherapy. Inclusion in the study required 1) a baseline LDL-C level between 160 and 400 mg/dL and 2) a medical history and clinical presentation consistent with HeFH. The mean baseline LDL-C value was 225 mg/dL (range: 161-351 mg/dL) in the ezetimibe coadministered with simvastatin group compared to 219 mg/dL (range: 149-336 mg/dL) in the simvastatin monotherapy group. The patients received coadministered ezetimibe and simvastatin (10 mg, 20 mg, or 40 mg) or simvastatin monotherapy (10 mg, 20 mg, or 40 mg) for 6 weeks, coadministered ezetimibe and 40 mg simvastatin or 40 mg simvastatin monotherapy for the next 27 weeks, and open-label coadministered ezetimibe and simvastatin (10 mg, 20 mg, or 40 mg) for 20 weeks thereafter.

The results of the study at Week 6 are summarized in Table 3. Results at Week 33 were consistent with those at Week 6.

Table 3: Mean Percent Difference at Week 6 Between the Pooled Ezetimibe Coadministered with Simvastatin Group and the Pooled Simvastatin Monotherapy Group in Adolescent Patients with Heterozygous Familial Hypercholesterolemia
 | Total-C | LDL-C | Apo B | Non-HDL-C | TG [For triglycerides, median % change from baseline] | HDL-C
Mean percent difference between treatment groups | -12% | -15% | -12% | -14% | -2% | +0.1%
95% Confidence Interval | (-15%, -9%) | (-18%, -12%) | (-15%, -9%) | (-17%, -11%) | (-9, +4) | (-3, +3)

From the start of the trial to the end of Week 33, discontinuations due to an adverse reaction occurred in 7 (6%) patients in the ezetimibe coadministered with simvastatin group and in 2 (2%) patients in the simvastatin monotherapy group.

During the trial, hepatic transaminase elevations (two consecutive measurements for ALT and/or AST ≥3 X ULN) occurred in four (3%) individuals in the ezetimibe coadministered with simvastatin group and in two (2%) individuals in the simvastatin monotherapy group. Elevations of CPK (≥10 X ULN) occurred in two (2%) individuals in the ezetimibe coadministered with simvastatin group and in zero individuals in the simvastatin monotherapy group.

In this limited controlled study, there was no significant effect on growth or sexual maturation in the adolescent boys or girls, or on menstrual cycle length in girls.

Coadministration of ezetimibe with simvastatin at doses greater than 40 mg/day has not been studied in adolescents. Also, VYTORIN has not been studied in patients younger than 10 years of age or in pre-menarchal girls.

Ezetimibe

Based on total ezetimibe (ezetimibe + ezetimibe-glucuronide) there are no pharmacokinetic differences between adolescents and adults. Pharmacokinetic data in the pediatric population <10 years of age are not available.

Simvastatin

The pharmacokinetics of simvastatin has not been studied in the pediatric population.

8.5 Geriatric Use

Of the 10,189 patients who received VYTORIN in clinical studies, 3242 (32%) were 65 and older (this included 844 (8%) who were 75 and older). No overall differences in safety or effectiveness were observed between these subjects and younger subjects, and other reported clinical experience has not identified differences in responses between the elderly and younger patients but greater sensitivity of some older individuals cannot be ruled out. Since advanced age (≥65 years) is a predisposing factor for myopathy, VYTORIN should be prescribed with caution in the elderly. [See Clinical Pharmacology (12.3).]

8.6 Renal Impairment

Caution should be exercised when VYTORIN is administered to patients with severe renal impairment. [See Dosage and Administration (2.4).]

8.7 Hepatic Impairment

VYTORIN is contraindicated in patients with active liver disease or unexplained persistent elevations of hepatic transaminases. VYTORIN is not recommended in patients with moderate to severe hepatic impairment. [See Contraindications (4) and Warnings and Precautions (5.2).]

10 OVERDOSAGE

VYTORIN

No specific treatment of overdosage with VYTORIN can be recommended. In the event of an overdose, symptomatic and supportive measures should be employed.

Ezetimibe

In clinical studies, administration of ezetimibe, 50 mg/day to 15 healthy subjects for up to 14 days, or 40 mg/day to 18 patients with primary hyperlipidemia for up to 56 days, was generally well tolerated.

A few cases of overdosage have been reported; most have not been associated with adverse experiences. Reported adverse experiences have not been serious.

Simvastatin

Significant lethality was observed in mice after a single oral dose of 9 g/m^2. No evidence of lethality was observed in rats or dogs treated with doses of 30 and 100 g/m^2, respectively. No specific diagnostic signs were observed in rodents. At these doses the only signs seen in dogs were emesis and mucoid stools.

A few cases of overdosage with simvastatin have been reported; the maximum dose taken was 3.6 g. All patients recovered without sequelae.

The dialyzability of simvastatin and its metabolites in man is not known at present.

11 DESCRIPTION

VYTORIN contains ezetimibe, a selective inhibitor of intestinal cholesterol and related phytosterol absorption, and simvastatin, an HMG-CoA reductase inhibitor.

The chemical name of ezetimibe is 1-(4-fluorophenyl)-3(R)-[3-(4-fluorophenyl)-3(S)-hydroxypropyl]-4(S)-(4-hydroxyphenyl)-2-azetidinone. The empirical formula is C24H21F2NO3 and its molecular weight is 409.4.

Ezetimibe is a white, crystalline powder that is freely to very soluble in ethanol, methanol, and acetone and practically insoluble in water. Its structural formula is:

Simvastatin, an inactive lactone, is hydrolyzed to the corresponding β-hydroxyacid form, which is an inhibitor of HMGCoA reductase. Simvastatin is butanoic acid, 2,2-dimethyl-,1,2,3,7,8,8a-hexahydro-3,7-dimethyl-8-[2-(tetrahydro-4-hydroxy-6-oxo-2H-pyran-2-yl)-ethyl]-1-naphthalenyl ester, [1S-[1α,3α,7β,8β(2S*,4S*),-8aβ]]. The empirical formula of simvastatin is C25H38O5 and its molecular weight is 418.57.

Simvastatin is a white to off-white, nonhygroscopic, crystalline powder that is practically insoluble in water and freely soluble in chloroform, methanol and ethanol. Its structural formula is:

VYTORIN is available for oral use as tablets containing 10 mg of ezetimibe, and 10 mg of simvastatin (VYTORIN 10/10), 20 mg of simvastatin (VYTORIN 10/20), 40 mg of simvastatin (VYTORIN 10/40), or 80 mg of simvastatin (VYTORIN 10/80). Each tablet contains the following inactive ingredients: butylated hydroxyanisole NF, citric acid monohydrate USP, croscarmellose sodium NF, hypromellose USP, lactose monohydrate NF, magnesium stearate NF, microcrystalline cellulose NF, and propyl gallate NF.

12 CLINICAL PHARMACOLOGY

12.1 Mechanism of Action

VYTORIN

Plasma cholesterol is derived from intestinal absorption and endogenous synthesis. VYTORIN contains ezetimibe and simvastatin, two lipid-lowering compounds with complementary mechanisms of action. VYTORIN reduces elevated total-C, LDL-C, Apo B, TG, and non-HDL-C, and increases HDL-C through dual inhibition of cholesterol absorption and synthesis.

Ezetimibe

Ezetimibe reduces blood cholesterol by inhibiting the absorption of cholesterol by the small intestine. The molecular target of ezetimibe has been shown to be the sterol transporter, Niemann-Pick C1-Like 1 (NPC1L1), which is involved in the intestinal uptake of cholesterol and phytosterols. In a 2-week clinical study in 18 hypercholesterolemic patients, ezetimibe inhibited intestinal cholesterol absorption by 54%, compared with placebo. Ezetimibe had no clinically meaningful effect on the plasma concentrations of the fat-soluble vitamins A, D, and E and did not impair adrenocortical steroid hormone production.

Ezetimibe localizes at the brush border of the small intestine and inhibits the absorption of cholesterol, leading to a decrease in the delivery of intestinal cholesterol to the liver. This causes a reduction of hepatic cholesterol stores and an increase in clearance of cholesterol from the blood; this distinct mechanism is complementary to that of statins [see Clinical Studies (14)].

Simvastatin

Simvastatin is a prodrug and is hydrolyzed to its active β-hydroxyacid form, simvastatin acid, after administration. Simvastatin is a specific inhibitor of 3-hydroxy-3-methylglutaryl-coenzyme A (HMG-CoA) reductase, the enzyme that catalyzes the conversion of HMG-CoA to mevalonate, an early and rate limiting step in the biosynthetic pathway for cholesterol. In addition, simvastatin reduces very-low-density lipoproteins (VLDL) and TG and increases HDL-C.

12.2 Pharmacodynamics

Clinical studies have demonstrated that elevated levels of total-C, LDL-C and Apo B, the major protein constituent of LDL, promote human atherosclerosis. In addition, decreased levels of HDL-C are associated with the development of atherosclerosis. Epidemiologic studies have established that cardiovascular morbidity and mortality vary directly with the level of total-C and LDL-C and inversely with the level of HDL-C. Like LDL, cholesterol-enriched triglyceride-rich lipoproteins, including VLDL, intermediate-density lipoproteins (IDL), and remnants, can also promote atherosclerosis. The independent effect of raising HDL-C or lowering TG on the risk of coronary and cardiovascular morbidity and mortality has not been determined.

12.3 Pharmacokinetics

The results of a bioequivalence study in healthy subjects demonstrated that the VYTORIN (ezetimibe/simvastatin) 10 mg/10 mg to 10 mg/80 mg combination tablets are bioequivalent to coadministration of corresponding doses of ezetimibe (ZETIA®) and simvastatin (ZOCOR®) as individual tablets.

Absorption

Ezetimibe

After oral administration, ezetimibe is absorbed and extensively conjugated to a pharmacologically active phenolic glucuronide (ezetimibe-glucuronide).

Simvastatin

The availability of the β-hydroxyacid to the systemic circulation following an oral dose of simvastatin was found to be less than 5% of the dose, consistent with extensive hepatic first-pass extraction.

Effect of Food on Oral Absorption

Ezetimibe

Concomitant food administration (high-fat or non-fat meals) had no effect on the extent of absorption of ezetimibe when administered as 10-mg tablets. The Cmax value of ezetimibe was increased by 38% with consumption of high-fat meals.

Simvastatin

Relative to the fasting state, the plasma profiles of both active and total inhibitors of HMG-CoA reductase were not affected when simvastatin was administered immediately before an American Heart Association recommended low-fat meal.

Distribution

Ezetimibe

Ezetimibe and ezetimibe-glucuronide are highly bound (>90%) to human plasma proteins.

Simvastatin

Both simvastatin and its β-hydroxyacid metabolite are highly bound (approximately 95%) to human plasma proteins. When radiolabeled simvastatin was administered to rats, simvastatin-derived radioactivity crossed the blood-brain barrier.

Metabolism and Excretion

Ezetimibe

Ezetimibe is primarily metabolized in the small intestine and liver via glucuronide conjugation with subsequent biliary and renal excretion. Minimal oxidative metabolism has been observed in all species evaluated.

In humans, ezetimibe is rapidly metabolized to ezetimibe-glucuronide. Ezetimibe and ezetimibe-glucuronide are the major drug-derived compounds detected in plasma, constituting approximately 10 to 20% and 80 to 90% of the total drug in plasma, respectively. Both ezetimibe and ezetimibe-glucuronide are eliminated from plasma with a half-life of approximately 22 hours for both ezetimibe and ezetimibe-glucuronide. Plasma concentration-time profiles exhibit multiple peaks, suggesting enterohepatic recycling.

Following oral administration of ^14C-ezetimibe (20 mg) to human subjects, total ezetimibe (ezetimibe + ezetimibe-glucuronide) accounted for approximately 93% of the total radioactivity in plasma. After 48 hours, there were no detectable levels of radioactivity in the plasma.

Approximately 78% and 11% of the administered radioactivity were recovered in the feces and urine, respectively, over a 10-day collection period. Ezetimibe was the major component in feces and accounted for 69% of the administered dose, while ezetimibe-glucuronide was the major component in urine and accounted for 9% of the administered dose.

Simvastatin

Simvastatin is a lactone that is readily hydrolyzed in vivo to the corresponding β-hydroxyacid, a potent inhibitor of HMG-CoA reductase. Inhibition of HMG-CoA reductase is a basis for an assay in pharmacokinetic studies of the β-hydroxyacid metabolites (active inhibitors) and, following base hydrolysis, active plus latent inhibitors (total inhibitors) in plasma following administration of simvastatin. The major active metabolites of simvastatin present in human plasma are the β-hydroxyacid of simvastatin and its 6′-hydroxy, 6′-hydroxymethyl, and 6′-exomethylene derivatives.

Following an oral dose of ^14C-labeled simvastatin in man, 13% of the dose was excreted in urine and 60% in feces. Plasma concentrations of total radioactivity (simvastatin plus ^14C-metabolites) peaked at 4 hours and declined rapidly to about 10% of peak by 12 hours postdose.

Specific Populations

Geriatric Patients

Ezetimibe

In a multiple-dose study with ezetimibe given 10 mg once daily for 10 days, plasma concentrations for total ezetimibe were about 2-fold higher in older (≥65 years) healthy subjects compared to younger subjects.

Simvastatin

In a study including 16 elderly patients between 70 and 78 years of age who received simvastatin 40 mg/day, the mean plasma level of HMG-CoA reductase inhibitory activity was increased approximately 45% compared with 18 patients between 18-30 years of age.

Pediatric Patients: [See Pediatric Use (8.4).]

Gender

Ezetimibe

In a multiple-dose study with ezetimibe given 10 mg once daily for 10 days, plasma concentrations for total ezetimibe were slightly higher (<20%) in women than in men.

Race

Ezetimibe

Based on a meta-analysis of multiple-dose pharmacokinetic studies, there were no pharmacokinetic differences between Black and Caucasian subjects. Studies in Asian subjects indicated that the pharmacokinetics of ezetimibe was similar to those seen in Caucasian subjects.

Hepatic Impairment

Ezetimibe

After a single 10-mg dose of ezetimibe, the mean exposure (based on area under the curve [AUC]) to total ezetimibe was increased approximately 1.7-fold in patients with mild hepatic impairment (Child-Pugh score 5 to 6), compared to healthy subjects. The mean AUC values for total ezetimibe and ezetimibe increased approximately 3- to 4-fold and 5- to 6-fold, respectively, in patients with moderate (Child-Pugh score 7 to 9) or severe hepatic impairment (Child-Pugh score 10 to 15). In a 14-day, multiple-dose study (10 mg daily) in patients with moderate hepatic impairment, the mean AUC for total ezetimibe and ezetimibe increased approximately 4-fold compared to healthy subjects.

Renal Impairment

Ezetimibe

After a single 10-mg dose of ezetimibe in patients with severe renal disease (n=8; mean CrCl ≤30 mL/min/1.73 m^2), the mean AUC for total ezetimibe and ezetimibe increased approximately 1.5-fold, compared to healthy subjects (n=9).

Simvastatin

Pharmacokinetic studies with another statin having a similar principal route of elimination to that of simvastatin have suggested that for a given dose level higher systemic exposure may be achieved in patients with severe renal impairment (as measured by creatinine clearance).

Drug Interactions [See also Drug Interactions (7).]

No clinically significant pharmacokinetic interaction was seen when ezetimibe was coadministered with simvastatin. No specific pharmacokinetic drug interaction studies with VYTORIN have been conducted other than the following study with NIASPAN (Niacin extended-release tablets).

Niacin: The effect of VYTORIN (10/20 mg daily for 7 days) on the pharmacokinetics of NIASPAN extended-release tablets (1000 mg for 2 days and 2000 mg for 5 days following a low-fat breakfast) was studied in healthy subjects. The mean Cmax and AUC of niacin increased 9% and 22%, respectively. The mean Cmax and AUC of nicotinuric acid increased 10% and 19%, respectively (N=13). In the same study, the effect of NIASPAN on the pharmacokinetics of VYTORIN was evaluated (N=15). While concomitant NIASPAN decreased the mean Cmax of total ezetimibe (1%), and simvastatin (2%), it increased the mean Cmax of simvastatin acid (18%). In addition, concomitant NIASPAN increased the mean AUC of total ezetimibe (26%), simvastatin (20%), and simvastatin acid (35%).

Cases of myopathy/rhabdomyolysis have been observed with simvastatin coadministered with lipid-modifying doses (≥1 g/day niacin) of niacin-containing products. [See Warnings and Precautions (5.1) and Drug Interactions (7.4).]

Cytochrome P450: Ezetimibe had no significant effect on a series of probe drugs (caffeine, dextromethorphan, tolbutamide, and IV midazolam) known to be metabolized by cytochrome P450 (1A2, 2D6, 2C8/9 and 3A4) in a “cocktail” study of twelve healthy adult males. This indicates that ezetimibe is neither an inhibitor nor an inducer of these cytochrome P450 isozymes, and it is unlikely that ezetimibe will affect the metabolism of drugs that are metabolized by these enzymes.

In a study of 12 healthy volunteers, simvastatin at the 80-mg dose had no effect on the metabolism of the probe cytochrome P450 isoform 3A4 (CYP3A4) substrates midazolam and erythromycin. This indicates that simvastatin is not an inhibitor of CYP3A4 and, therefore, is not expected to affect the plasma levels of other drugs metabolized by CYP3A4.

Although the mechanism is not fully understood, cyclosporine has been shown to increase the AUC of statins. The increase in AUC for simvastatin acid is presumably due, in part, to inhibition of CYP3A4.

Simvastatin is a substrate for CYP3A4. Inhibitors of CYP3A4 can raise the plasma levels of HMG-CoA reductase inhibitory activity and increase the risk of myopathy. [See Warnings and Precautions (5.1); Drug Interactions (7.1).]

Ezetimibe

Table 4: Effect of Coadministered Drugs on Total Ezetimibe
Coadministered Drug and Dosing Regimen | Total Ezetimibe [Based on 10 mg-dose of ezetimibe]
Coadministered Drug and Dosing Regimen | Change in AUC | Change in Cmax
Cyclosporine-stable dose required (75-150 mg BID) [Post-renal transplant patients with mild impaired or normal renal function. In a different study, a renal transplant patient with severe renal insufficiency (creatinine clearance of 13.2 mL/min/1.73 m^2) who was receiving multiple medications, including cyclosporine, demonstrated a 12-fold greater exposure to total ezetimibe compared to healthy subjects.] , [See 7. Drug Interactions] | ↑240% | ↑290%
Fenofibrate, 200 mg QD, 14 days | ↑48% | ↑64%
Gemfibrozil, 600 mg BID, 7 days | ↑64% | ↑91%
Cholestyramine, 4 g BID, 14 days | ↓55% | ↓4%
Aluminum & magnesium hydroxide combination antacid, single dose [Supralox®, 20 mL] | ↓4% | ↓30%
Cimetidine, 400 mg BID, 7 days | ↑6% | ↑22%
Glipizide, 10 mg, single dose | ↑4% | ↓8%
Statins
Lovastatin 20 mg QD, 7 days | ↑9% | ↑3%
Pravastatin 20 mg QD, 14 days | ↑7% | ↑23%
Atorvastatin 10 mg QD, 14 days | ↓2% | ↑12%
Rosuvastatin 10 mg QD, 14 days | ↑13% | ↑18%
Fluvastatin 20 mg QD, 14 days | ↓19% | ↑7%

Table 5: Effect of Ezetimibe Coadministration on Systemic Exposure to Other Drugs
Coadministered Drug and its Dosage Regimen | Ezetimibe Dosage Regimen | Change in AUC; of Coadministered Drug | Change in Cmax; of Coadministered Drug
Warfarin, 25 mg single dose on Day 7 | 10 mg QD, 11 days | ↓2% (R-warfarin); ↓4% (S-warfarin) | ↑3% (R-warfarin); ↑1% (S-warfarin)
Digoxin, 0.5 mg single dose | 10 mg QD, 8 days | ↑2% | ↓7%
Gemfibrozil, 600 mg BID, 7 days [See 7. Drug Interactions] | 10 mg QD, 7 days | ↓1% | ↓11%
Ethinyl estradiol & Levonorgestrel QD, 21 days | 10 mg QD, Days 8-14 of 21 day oral contraceptive cycle | Ethinyl estradiol; 0%; Levonorgestrel; 0% | Ethinyl estradiol; ↓9%; Levonorgestrel; ↓5%
Glipizide, 10 mg on Days 1 and 9 | 10 mg QD, Days 2-9 | ↓3% | ↓5%
Fenofibrate, 200 mg QD, 14 days | 10 mg QD, 14 days | ↑11% | ↑7%
Cyclosporine, 100 mg single dose Day 7 | 20 mg QD, 8 days | ↑15% | ↑10%
Statins
Lovastatin 20 mg QD, 7 days | 10 mg QD, 7 days | ↑19% | ↑3%
Pravastatin 20 mg QD, 14 days | 10 mg QD, 14 days | ↓20% | ↓24%
Atorvastatin 10 mg QD, 14 days | 10 mg QD, 14 days | ↓4% | ↑7%
Rosuvastatin 10 mg QD, 14 days | 10 mg QD, 14 days | ↑19% | ↑17%
Fluvastatin 20 mg QD, 14 days | 10 mg QD, 14 days | ↓39% | ↓27%

Simvastatin

Table 6: Effect of Coadministered Drugs or Grapefruit Juice on Simvastatin Systemic Exposure
Coadministered Drug or Grapefruit Juice | Dosing of Coadministered Drug or Grapefruit Juice | Dosing of Simvastatin | Geometric Mean Ratio; (Ratio [Results based on a chemical assay except results with propranolol as indicated.] with / without coadministered drug); No Effect = 1.00
Coadministered Drug or Grapefruit Juice | Dosing of Coadministered Drug or Grapefruit Juice | Dosing of Simvastatin |  | AUC | Cmax
Avoid taking with VYTORIN [see Warnings and Precautions (5.1)]
Telithromycin [Results could be representative of the following CYP3A4 inhibitors: ketoconazole, erythromycin, clarithromycin, HIV protease inhibitors, and nefazodone.] | 200 mg QD for 4 days | 80 mg | simvastatin acid [Simvastatin acid refers to the β-hydroxyacid of simvastatin.] simvastatin | 12 8.9 | 15 5.3
Nelfinavir | 1250 mg BID for 14 days | 20 mg QD for 28 days | simvastatin acid simvastatin | 6 | 6.2
Itraconazole | 200 mg QD for 4 days | 80 mg | simvastatin acid simvastatin |  | 13.1; 13.1
Avoid >1 quart of grapefruit juice with VYTORIN [see Warnings and Precautions (5.1)]
Grapefruit Juice [The effect of amounts of grapefruit juice between those used in these two studies on simvastatin pharmacokinetics has not been studied.]; (high dose) | 200 mL of double-strength TID [Double-strength: one can of frozen concentrate diluted with one can of water. Grapefruit juice was administered TID for 2 days, and 200 mL together with single dose simvastatin and 30 and 90 minutes following single dose simvastatin on Day 3.] | 60 mg single dose | simvastatin acid simvastatin | 7 16
Grapefruit Juice; (low dose) | 8 oz (about 237 mL) of single-strength [Single-strength: one can of frozen concentrate diluted with 3 cans of water. Grapefruit juice was administered with breakfast for 3 days, and simvastatin was administered in the evening on Day 3.] | 20 mg single dose | simvastatin acid simvastatin | 1.3 1.9
Avoid taking with VYTORIN. If VYTORIN is used in combination with gemfibrozil, the dose should not exceed 10/10 mg daily, based on clinical and/or post-marketing simvastatin experience [see Warnings and Precautions (5.1)]
Gemfibrozil | 600 mg BID for 3 days | 40 mg | simvastatin acid simvastatin | 2.85 1.35 | 2.18 0.91
Avoid taking with >10/20 mg VYTORIN, based on clinical and/or post-marketing simvastatin experience [see Warnings and Precautions (5.1)]
Verapamil SR | 240 mg QD Days 1-7 then 240 mg BID on Days 8-10 | 80 mg on Day 10 | simvastatin acid simvastatin | 2.3 2.5 | 2.4 2.1
Avoid taking with >10/40 mg VYTORIN, based on clinical and/or post-marketing simvastatin experience [see Warnings and Precautions (5.1)]
Diltiazem | 120 mg BID for 10 days | 80 mg on Day 10 | simvastatin acid simvastatin | 2.69 3.10 | 2.69 2.88
Diltiazem | 120 mg BID for 14 days | 20 mg on Day 14 | simvastatin | 4.6 | 3.6
No dosing adjustments required for the following:
Fenofibrate | 160 mg QD x14 days | 80 mg QD on Days 8-14 | simvastatin acid simvastatin | 0.64 0.89 | 0.89 0.83
Amlodipine | 10 mg QD x 10 days | 80 mg on Day 10 | simvastatin acid simvastatin | 1.58 1.77 | 1.56 1.47
Propranolol | 80 mg single dose | 80 mg single dose | total inhibitor active inhibitor | 0.79 0.79 | ↓ from 33.6 to 21.1 ng·eq/ml ↓ from 7.0 to 4.7 ng·eq/mL

13 NONCLINICAL TOXICOLOGY

13.1 Carcinogenesis, Mutagenesis, Impairment of Fertility

VYTORIN

No animal carcinogenicity or fertility studies have been conducted with the combination of ezetimibe and simvastatin. The combination of ezetimibe with simvastatin did not show evidence of mutagenicity in vitro in a microbial mutagenicity (Ames) test with Salmonella typhimurium and Escherichia coli with or without metabolic activation. No evidence of clastogenicity was observed in vitro in a chromosomal aberration assay in human peripheral blood lymphocytes with ezetimibe and simvastatin with or without metabolic activation. There was no evidence of genotoxicity at doses up to 600 mg/kg with the combination of ezetimibe and simvastatin (1:1) in the in vivo mouse micronucleus test.

Ezetimibe

A 104-week dietary carcinogenicity study with ezetimibe was conducted in rats at doses up to 1500 mg/kg/day (males) and 500 mg/kg/day (females) (~20 times the human exposure at 10 mg daily based on AUC0-24hr for total ezetimibe). A 104-week dietary carcinogenicity study with ezetimibe was also conducted in mice at doses up to 500 mg/kg/day (>150 times the human exposure at 10 mg daily based on AUC0-24hr for total ezetimibe). There were no statistically significant increases in tumor incidences in drug-treated rats or mice.

No evidence of mutagenicity was observed in vitro in a microbial mutagenicity (Ames) test with Salmonella typhimurium and Escherichia coli with or without metabolic activation. No evidence of clastogenicity was observed in vitro in a chromosomal aberration assay in human peripheral blood lymphocytes with or without metabolic activation. In addition, there was no evidence of genotoxicity in the in vivo mouse micronucleus test.

In oral (gavage) fertility studies of ezetimibe conducted in rats, there was no evidence of reproductive toxicity at doses up to 1000 mg/kg/day in male or female rats (~7 times the human exposure at 10 mg daily based on AUC0-24hr for total ezetimibe).

Simvastatin

In a 72-week carcinogenicity study, mice were administered daily doses of simvastatin of 25, 100, and 400 mg/kg body weight, which resulted in mean plasma drug levels approximately 1, 4, and 8 times higher than the mean human plasma drug level, respectively, (as total inhibitory activity based on AUC) after an 80-mg oral dose. Liver carcinomas were significantly increased in high-dose females and mid- and high-dose males with a maximum incidence of 90% in males. The incidence of adenomas of the liver was significantly increased in mid- and high-dose females. Drug treatment also significantly increased the incidence of lung adenomas in mid- and high-dose males and females. Adenomas of the Harderian gland (a gland of the eye of rodents) were significantly higher in high-dose mice than in controls. No evidence of a tumorigenic effect was observed at 25 mg/kg/day.

In a separate 92-week carcinogenicity study in mice at doses up to 25 mg/kg/day, no evidence of a tumorigenic effect was observed (mean plasma drug levels were 1 times higher than humans given 80 mg simvastatin as measured by AUC).

In a two-year study in rats at 25 mg/kg/day, there was a statistically significant increase in the incidence of thyroid follicular adenomas in female rats exposed to approximately 11 times higher levels of simvastatin than in humans given 80 mg simvastatin (as measured by AUC).

A second two-year rat carcinogenicity study with doses of 50 and 100 mg/kg/day produced hepatocellular adenomas and carcinomas (in female rats at both doses and in males at 100 mg/kg/day). Thyroid follicular cell adenomas were increased in males and females at both doses; thyroid follicular cell carcinomas were increased in females at 100 mg/kg/day. The increased incidence of thyroid neoplasms appears to be consistent with findings from other statins. These treatment levels represented plasma drug levels (AUC) of approximately 7 and 15 times (males) and 22 and 25 times (females) the mean human plasma drug exposure after an 80-mg daily dose.

No evidence of mutagenicity was observed in a microbial mutagenicity (Ames) test with or without rat or mouse liver metabolic activation. In addition, no evidence of damage to genetic material was noted in an in vitro alkaline elution assay using rat hepatocytes, a V-79 mammalian cell forward mutation study, an in vitro chromosome aberration study in CHO cells, or an in vivo chromosomal aberration assay in mouse bone marrow.

There was decreased fertility in male rats treated with simvastatin for 34 weeks at 25 mg/kg body weight (4 times the maximum human exposure level, based on AUC, in patients receiving 80 mg/day); however, this effect was not observed during a subsequent fertility study in which simvastatin was administered at this same dose level to male rats for 11 weeks (the entire cycle of spermatogenesis including epididymal maturation). No microscopic changes were observed in the testes of rats from either study. At 180 mg/kg/day, (which produces exposure levels 22 times higher than those in humans taking 80 mg/day based on surface area, mg/m^2), seminiferous tubule degeneration (necrosis and loss of spermatogenic epithelium) was observed. In dogs, there was drug-related testicular atrophy, decreased spermatogenesis, spermatocytic degeneration and giant cell formation at 10 mg/kg/day (approximately 2 times the human exposure, based on AUC, at 80 mg/day). The clinical significance of these findings is unclear.

13.2 Animal Toxicology and/or Pharmacology

CNS Toxicity

Optic nerve degeneration was seen in clinically normal dogs treated with simvastatin for 14 weeks at 180 mg/kg/day, a dose that produced mean plasma drug levels about 12 times higher than the mean plasma drug level in humans taking 80 mg/day.

A chemically similar drug in this class also produced optic nerve degeneration (Wallerian degeneration of retinogeniculate fibers) in clinically normal dogs in a dose-dependent fashion starting at 60 mg/kg/day, a dose that produced mean plasma drug levels about 30 times higher than the mean plasma drug level in humans taking the highest recommended dose (as measured by total enzyme inhibitory activity). This same drug also produced vestibulocochlear Wallerian-like degeneration and retinal ganglion cell chromatolysis in dogs treated for 14 weeks at 180 mg/kg/day, a dose that resulted in a mean plasma drug level similar to that seen with the 60 mg/kg/day dose.

CNS vascular lesions, characterized by perivascular hemorrhage and edema, mononuclear cell infiltration of perivascular spaces, perivascular fibrin deposits and necrosis of small vessels were seen in dogs treated with simvastatin at a dose of 360 mg/kg/day, a dose that produced mean plasma drug levels that were about 14 times higher than the mean plasma drug levels in humans taking 80 mg/day. Similar CNS vascular lesions have been observed with several other drugs of this class.

There were cataracts in female rats after two years of treatment with 50 and 100 mg/kg/day (22 and 25 times the human AUC at 80 mg/day, respectively) and in dogs after three months at 90 mg/kg/day (19 times) and at two years at 50 mg/kg/day (5 times).

Ezetimibe

The hypocholesterolemic effect of ezetimibe was evaluated in cholesterol-fed Rhesus monkeys, dogs, rats, and mouse models of human cholesterol metabolism. Ezetimibe was found to have an ED50 value of 0.5 μg/kg/day for inhibiting the rise in plasma cholesterol levels in monkeys. The ED50 values in dogs, rats, and mice were 7, 30, and 700 μg/kg/day, respectively. These results are consistent with ezetimibe being a potent cholesterol absorption inhibitor.

In a rat model, where the glucuronide metabolite of ezetimibe (ezetimibe-glucuronide) was administered intraduodenally, the metabolite was as potent as ezetimibe in inhibiting the absorption of cholesterol, suggesting that the glucuronide metabolite had activity similar to the parent drug.

In 1-month studies in dogs given ezetimibe (0.03 to 300 mg/kg/day), the concentration of cholesterol in gallbladder bile increased ~2- to 4-fold. However, a dose of 300 mg/kg/day administered to dogs for one year did not result in gallstone formation or any other adverse hepatobiliary effects. In a 14-day study in mice given ezetimibe (0.3 to 5 mg/kg/day) and fed a low-fat or cholesterol-rich diet, the concentration of cholesterol in gallbladder bile was either unaffected or reduced to normal levels, respectively.

A series of acute preclinical studies was performed to determine the selectivity of ezetimibe for inhibiting cholesterol absorption. Ezetimibe inhibited the absorption of ^14C-cholesterol with no effect on the absorption of triglycerides, fatty acids, bile acids, progesterone, ethinyl estradiol, or the fat-soluble vitamins A and D.

In 4- to 12-week toxicity studies in mice, ezetimibe did not induce cytochrome P450 drug-metabolizing enzymes. In toxicity studies, a pharmacokinetic interaction of ezetimibe with statins (parents or their active hydroxy acid metabolites) was seen in rats, dogs, and rabbits.

14 CLINICAL STUDIES

14.1 Primary Hyperlipidemia

VYTORIN

VYTORIN reduces total-C, LDL-C, Apo B, TG, and non-HDL-C, and increases HDL-C in patients with hyperlipidemia. Maximal to near maximal response is generally achieved within 2 weeks and maintained during chronic therapy.

VYTORIN is effective in men and women with hyperlipidemia. Experience in non-Caucasians is limited and does not permit a precise estimate of the magnitude of the effects of VYTORIN.

Five multicenter, double-blind studies conducted with either VYTORIN or coadministered ezetimibe and simvastatin equivalent to VYTORIN in patients with primary hyperlipidemia are reported: two were comparisons with simvastatin, two were comparisons with atorvastatin, and one was a comparison with rosuvastatin.

In a multicenter, double-blind, placebo-controlled, 12-week trial, 1528 hyperlipidemic patients were randomized to one of ten treatment groups: placebo, ezetimibe (10 mg), simvastatin (10 mg, 20 mg, 40 mg, or 80 mg), or VYTORIN (10/10, 10/20, 10/40, or 10/80).

When patients receiving VYTORIN were compared to those receiving all doses of simvastatin, VYTORIN significantly lowered total-C, LDL-C, Apo B, TG, and non-HDL-C. The effects of VYTORIN on HDL-C were similar to the effects seen with simvastatin. Further analysis showed VYTORIN significantly increased HDL-C compared with placebo. (See Table 7.) The lipid response to VYTORIN was similar in patients with TG levels greater than or less than 200 mg/dL.

Table 7: Response to VYTORIN in Patients with Primary Hyperlipidemia (Mean [For triglycerides, median % change from baseline] % Change from Untreated Baseline [Baseline - on no lipid-lowering drug])
Treatment (Daily Dose) | N | Total-C | LDL-C | Apo B | HDL-C | TG | Non-HDL-C
Pooled data (All VYTORIN doses) [VYTORIN doses pooled (10/10-10/80) significantly reduced total-C, LDL-C, Apo B, TG, and non-HDL-C compared to simvastatin and significantly increased HDL-C compared to placebo.] | 609 | -38 | -53 | -42 | +7 | -24 | -49
Pooled data (All simvastatin doses) | 622 | -28 | -39 | -32 | +7 | -21 | -36
Ezetimibe 10 mg | 149 | -13 | -19 | -15 | +5 | -11 | -18
Placebo | 148 | -1 | -2 | 0 | 0 | -2 | -2
VYTORIN by dose
10/10 | 152 | -31 | -45 | -35 | +8 | -23 | -41
10/20 | 156 | -36 | -52 | -41 | +10 | -24 | -47
10/40 | 147 | -39 | -55 | -44 | +6 | -23 | -51
10/80 | 154 | -43 | -60 | -49 | +6 | -31 | -56
Simvastatin by dose
10 mg | 158 | -23 | -33 | -26 | +5 | -17 | -30
20 mg | 150 | -24 | -34 | -28 | +7 | -18 | -32
40 mg | 156 | -29 | -41 | -33 | +8 | -21 | -38
80 mg | 158 | -35 | -49 | -39 | +7 | -27 | -45

In a multicenter, double-blind, controlled, 23-week study, 710 patients with known CHD or CHD risk equivalents, as defined by the NCEP ATP III guidelines, and an LDL-C ≥130 mg/dL were randomized to one of four treatment groups: coadministered ezetimibe and simvastatin equivalent to VYTORIN (10/10, 10/20, and 10/40) or simvastatin 20 mg. Patients not reaching an LDL-C <100 mg/dL had their simvastatin dose titrated at 6-week intervals to a maximal dose of 80 mg.

At Week 5, the LDL-C reductions with VYTORIN 10/10, 10/20, or 10/40 were significantly larger than with simvastatin 20 mg (see Table 8).

Table 8: Response to VYTORIN after 5 Weeks in Patients with CHD or CHD Risk Equivalents and an LDL-C ≥130 mg/dL
 | Simvastatin 20 mg | VYTORIN 10/10 | VYTORIN 10/20 | VYTORIN 10/40
N | 253 | 251 | 109 | 97
Mean baseline LDL-C | 174 | 165 | 167 | 171
Percent change LDL-C | -38 | -47 | -53 | -59

In a multicenter, double-blind, 6-week study, 1902 patients with primary hyperlipidemia, who had not met their NCEP ATP III target LDL-C goal, were randomized to one of eight treatment groups: VYTORIN (10/10, 10/20, 10/40, or 10/80) or atorvastatin (10 mg, 20 mg, 40 mg, or 80 mg).

Across the dosage range, when patients receiving VYTORIN were compared to those receiving milligram-equivalent statin doses of atorvastatin, VYTORIN lowered total-C, LDL-C, Apo B, and non-HDL-C significantly more than atorvastatin. Only the 10/40 mg and 10/80 mg VYTORIN doses increased HDL-C significantly more than the corresponding milligram-equivalent statin dose of atorvastatin. The effects of VYTORIN on TG were similar to the effects seen with atorvastatin. (See Table 9.)

Table 9: Response to VYTORIN and Atorvastatin in Patients with Primary Hyperlipidemia (Mean [For triglycerides, median % change from baseline] % Change from Untreated Baseline [Baseline - on no lipid-lowering drug])
Treatment (Daily Dose) | N | Total-C [VYTORIN doses pooled (10/10-10/80) provided significantly greater reductions in total-C, LDL-C, Apo B, and non-HDL-C compared to atorvastatin doses pooled (10-80).] | LDL-C | Apo B | HDL-C | TG | Non-HDL-C
VYTORIN by dose
10/10 | 230 | -34 [p<0.05 for difference with atorvastatin at equal mg doses of the simvastatin component] | -47 | -37 | +8 | -26 | -43
10/20 | 233 | -37 | -51 | -40 | +7 | -25 | -46
10/40 | 236 | -41 | -57 | -46 | +9 | -27 | -52
10/80 | 224 | -43 | -59 | -48 | +8 | -31 | -54
Atorvastatin by dose
10 mg | 235 | -27 | -36 | -31 | +7 | -21 | -34
20 mg | 230 | -32 | -44 | -37 | +5 | -25 | -41
40 mg | 232 | -36 | -48 | -40 | +4 | -24 | -45
80 mg | 230 | -40 | -53 | -44 | +1 | -32 | -50

In a multicenter, double-blind, 24-week, forced-titration study, 788 patients with primary hyperlipidemia, who had not met their NCEP ATP III target LDL-C goal, were randomized to receive coadministered ezetimibe and simvastatin equivalent to VYTORIN (10/10 and 10/20) or atorvastatin 10 mg. For all three treatment groups, the dose of the statin was titrated at 6-week intervals to 80 mg. At each pre-specified dose comparison, VYTORIN lowered LDL-C to a greater degree than atorvastatin (see Table 10).

Table 10: Response to VYTORIN and Atorvastatin in Patients with Primary Hyperlipidemia (Mean [For triglycerides, median % change from baseline] % Change from Untreated Baseline [Baseline - on no lipid-lowering drug])
Treatment | N | Total-C | LDL-C | Apo B | HDL-C | TG | Non-HDL-C
Week 6
Atorvastatin 10 mg [Atorvastatin: 10 mg start dose titrated to 20 mg, 40 mg, and 80 mg through Weeks 6, 12, 18, and 24] | 262 | -28 | -37 | -32 | +5 | -23 | -35
VYTORIN10/10 [VYTORIN: 10/10 start dose titrated to 10/20, 10/40, and 10/80 through Weeks 6, 12, 18, and 24] | 263 | -34 [p≤0.05 for difference with atorvastatin in the specified week] | -46 | -38 | +8 | -26 | -43
VYTORIN 10/20 [VYTORIN: 10/20 start dose titrated to 10/40, 10/40, and 10/80 through Weeks 6, 12, 18, and 24] | 263 | -36 | -50 | -41 | +10 | -25 | -46
Week 12
Atorvastatin 20 mg | 246 | -33 | -44 | -38 | +7 | -28 | -42
VYTORIN 10/20 | 250 | -37 | -50 | -41 | +9 | -28 | -46
VYTORIN 10/40 | 252 | -39 | -54 | -45 | +12 | -31 | -50
Week 18
Atorvastatin 40 mg | 237 | -37 | -49 | -42 | +8 | -31 | -47
VYTORIN 10/40 [Data pooled for common doses of VYTORIN at Weeks 18 and 24.] | 482 | -40 | -56 | -45 | +11 | -32 | -52
Week 24
Atorvastatin 80 mg | 228 | -40 | -53 | -45 | +6 | -35 | -50
VYTORIN 10/80 | 459 | -43 | -59 | -49 | +12 | -35 | -55

In a multicenter, double-blind, 6-week study, 2959 patients with primary hyperlipidemia, who had not met their NCEP ATP III target LDL-C goal, were randomized to one of six treatment groups: VYTORIN (10/20, 10/40, or 10/80) or rosuvastatin (10 mg, 20 mg, or 40 mg).

The effects of VYTORIN and rosuvastatin on total-C, LDL-C, Apo B, TG, non-HDL-C and HDL-C are shown in Table 11.

Table 11: Response to VYTORIN and Rosuvastatin in Patients with Primary Hyperlipidemia (Mean [For triglycerides, median % change from baseline] % Change from Untreated Baseline [Baseline - on no lipid-lowering drug])
Treatment (Daily Dose) | N | Total-C [VYTORIN doses pooled (10/20-10/80) provided significantly greater reductions in total-C, LDL-C, Apo B, and non-HDL-C compared to rosuvastatin doses pooled (10-40 mg).] | LDL-C | Apo B | HDL-C | TG | Non-HDL-C
VYTORIN by dose 10/20 | 476 | -37 [p<0.05 vs. rosuvastatin 10 mg] | -52 | -42 | +7 | -23 | -47
10/40 | 477 | -39 [p<0.05 vs. rosuvastatin 20 mg] | -55 | -44 | +8 | -27 | -50
10/80 | 474 | -44 [p<0.05 vs. rosuvastatin 40 mg] | -61 | -50 | +8 | -30 | -56
Rosuvastatin by dose 10 mg | 475 | -32 | -46 | -37 | +7 | -20 | -42
20 mg | 478 | -37 | -52 | -43 | +8 | -26 | -48
40 mg | 475 | -41 | -57 | -47 | +8 | -28 | -52

In a multicenter, double-blind, 24-week trial, 214 patients with type 2 diabetes mellitus treated with thiazolidinediones (rosiglitazone or pioglitazone) for a minimum of 3 months and simvastatin 20 mg for a minimum of 6 weeks were randomized to receive either simvastatin 40 mg or the coadministered active ingredients equivalent to VYTORIN 10/20. The median LDL-C and HbA1c levels at baseline were 89 mg/dL and 7.1%, respectively.

VYTORIN 10/20 was significantly more effective than doubling the dose of simvastatin to 40 mg. The median percent changes from baseline for VYTORIN vs. simvastatin were: LDL-C -25% and -5%; total-C -16% and -5%; Apo B -19% and -5%; and non-HDL-C -23% and -5%. Results for HDL-C and TG between the two treatment groups were not significantly different.

Ezetimibe

In two multicenter, double-blind, placebo-controlled, 12-week studies in 1719 patients with primary hyperlipidemia, ezetimibe significantly lowered total-C (-13%), LDL-C (-19%), Apo B (-14%), and TG (-8%), and increased HDL-C (+3%) compared to placebo. Reduction in LDL-C was consistent across age, sex, and baseline LDL-C.

Simvastatin

In two large, placebo-controlled clinical trials, the Scandinavian Simvastatin Survival Study (N=4,444 patients) and the Heart Protection Study (N=20,536 patients), the effects of treatment with simvastatin were assessed in patients at high risk of coronary events because of existing coronary heart disease, diabetes, peripheral vessel disease, history of stroke or other cerebrovascular disease. Simvastatin was proven to reduce: the risk of total mortality by reducing CHD deaths; the risk of non-fatal myocardial infarction and stroke; and the need for coronary and non-coronary revascularization procedures.

No incremental benefit of VYTORIN on cardiovascular morbidity and mortality over and above that demonstrated for simvastatin has been established.

14.2 Homozygous Familial Hypercholesterolemia (HoFH)

A double-blind, randomized, 12-week study was performed in patients with a clinical and/or genotypic diagnosis of HoFH. Data were analyzed from a subgroup of patients (n=14) receiving simvastatin 40 mg at baseline. Increasing the dose of simvastatin from 40 to 80 mg (n=5) produced a reduction of LDL-C of 13% from baseline on simvastatin 40 mg. Coadministered ezetimibe and simvastatin equivalent to VYTORIN (10/40 and 10/80 pooled, n=9), produced a reduction of LDL-C of 23% from baseline on simvastatin 40 mg. In those patients coadministered ezetimibe and simvastatin equivalent to VYTORIN (10/80, n=5), a reduction of LDL-C of 29% from baseline on simvastatin 40 mg was produced.

16 HOW SUPPLIED/STORAGE AND HANDLING

No. 3874 — Tablets VYTORIN 10/20 are white to off-white capsule-shaped tablets with code “312” on one side.

They are supplied as follows:

NDC 21695-325-30 bottles of 30

No. 3875 — Tablets VYTORIN 10/40 are white to off-white capsule-shaped tablets with code “313” on one side.

They are supplied as follows:

NDC 21695-339-30 bottles of 30

No. 3876 — Tablets VYTORIN 10/80 are white to off-white capsule-shaped tablets with code “315” on one side.

They are supplied as follows:

NDC 21695-827-30 bottles of 30

Storage

Store at 20-25°C (68-77°F). [See USP Controlled Room Temperature.] Keep container tightly closed.

Storage of 10,000, 5000, and 2500 count bottles

Store bottle of 10,000 VYTORIN 10/10 and 10/20, 5000 VYTORIN 10/40, and 2500 VYTORIN 10/80 capsule-shaped tablets at 20-25°C (68-77°F). [See USP Controlled Room Temperature.] Store in original container until time of use. When product container is subdivided, repackage into a tightly-closed, light-resistant container. Entire contents must be repackaged immediately upon opening.

Manufactured for:
MERCK/Schering-Plough Pharmaceuticals
North Wales, PA 19454, USA

By:
MSD Technology Singapore Pte. Ltd.
Singapore 637766

Or

Merck Sharp & Dohme (Italia) S.p.A.
Via Emilia, 21
27100 – Pavia, Italy

Or

Merck Sharp & Dohme Ltd.
Cramlington, Northumberland, UK NE23 3JU

Or

Jointly manufactured by:
Merck Sharp & Dohme (Italia) S.p.A.
Via Emilia, 21
27100 – Pavia, Italy
and
MSD Technology Singapore Pte. Ltd.
Singapore 637766

U.S. Patent Nos. 5,846,966 and RE37,721

Repackaged by:

Rebel Distributors Corp

Thousand Oaks, CA 91320

17 PATIENT COUNSELING INFORMATION

[See FDA-Approved Patient Labeling (17.5).]

Patients should be advised to adhere to their National Cholesterol Education Program (NCEP)-recommended diet, a regular exercise program, and periodic testing of a fasting lipid panel.

Patients should be advised about substances they should not take concomitantly with VYTORIN [see Warnings and Precautions (5.1)]. Patients should also be advised to inform other physicians prescribing a new medication that they are taking VYTORIN.

17.1 Muscle Pain

All patients starting therapy with VYTORIN should be advised of the risk of myopathy and told to report promptly any unexplained muscle pain, tenderness or weakness. The risk of this occurring is increased when taking certain types of medication or consuming larger quantities of grapefruit juice. They should discuss all medication, both prescription and over the counter, with their healthcare professional.

17.2 Liver Enzymes

It is recommended that liver function tests be performed before the initiation of VYTORIN, and thereafter when clinically indicated. Patients titrated to the 10/80-mg dose should receive an additional test prior to titration, 3 months after titration to the 10/80-mg dose, and periodically thereafter (e.g., semiannually) for the first year of treatment.

17.3 Pregnancy

Women of childbearing age should be advised to use an effective method of birth control to prevent pregnancy while using VYTORIN. Discuss future pregnancy plans with your patients, and discuss when to stop taking VYTORIN if they are trying to conceive. Patients should be advised that if they become pregnant they should stop taking VYTORIN and call their healthcare professional.

17.4 Breast-feeding

Women who are breast-feeding should be advised to not use VYTORIN. Patients who have a lipid disorder and are breast-feeding should be advised to discuss the options with their healthcare professional.

PATIENT INFORMATION

VYTORIN® (ezetimibe/simvastatin) Tablets
Patient Information about VYTORIN (VI-tor-in)
Generic name: ezetimibe/simvastatin tablets

Read this information carefully before you start taking VYTORIN. Review this information each time you refill your prescription for VYTORIN as there may be new information. This information does not take the place of talking with your doctor about your medical condition or your treatment. If you have any questions about VYTORIN, ask your doctor. Only your doctor can determine if VYTORIN is right for you.

What is VYTORIN?

VYTORIN contains two cholesterol-lowering medications, ezetimibe and simvastatin, available as a tablet in four strengths:

- VYTORIN 10/10 (ezetimibe 10 mg/simvastatin 10 mg)
- VYTORIN 10/20 (ezetimibe 10 mg/simvastatin 20 mg)
- VYTORIN 10/40 (ezetimibe 10 mg/simvastatin 40 mg)
- VYTORIN 10/80 (ezetimibe 10 mg/simvastatin 80 mg)

VYTORIN is a medicine used to lower levels of total cholesterol, LDL (bad) cholesterol, and fatty substances called triglycerides in the blood. In addition, VYTORIN raises levels of HDL (good) cholesterol. VYTORIN is for patients who cannot control their cholesterol levels by diet and exercise alone. You should stay on a cholesterol-lowering diet while taking this medicine.

VYTORIN works to reduce your cholesterol in two ways. It reduces the cholesterol absorbed in your digestive tract, as well as the cholesterol your body makes by itself. VYTORIN does not help you lose weight. VYTORIN has not been shown to reduce heart attacks or strokes more than simvastatin alone.

For more information about cholesterol, see the section called “What should I know about high cholesterol?”

Who should not take VYTORIN?

Do not take VYTORIN:

- If you are allergic to ezetimibe or simvastatin, the active ingredients in VYTORIN, or to the inactive ingredients. For a list of inactive ingredients, see the “Inactive ingredients” section at the end of this information sheet.
- If you have active liver disease or repeated blood tests indicating possible liver problems.
- If you are pregnant, or think you may be pregnant, or planning to become pregnant or breast-feeding.
- If you are a woman of childbearing age, you should use an effective method of birth control to prevent pregnancy while using VYTORIN.

VYTORIN has not been studied in children under 10 years of age.

What should I tell my doctor before and while taking VYTORIN?

Tell your doctor right away if you experience unexplained muscle pain, tenderness, or weakness. This is because on rare occasions, muscle problems can be serious, including muscle breakdown resulting in kidney damage.

The risk of muscle breakdown is greater at higher doses of VYTORIN.

The risk of muscle breakdown is greater in patients with kidney problems.

Taking VYTORIN with certain substances can increase the risk of muscle problems. It is particularly important to tell your doctor if you are taking any of the following:

- cyclosporine
- danazol
- antifungal agents (such as itraconazole or ketoconazole)
- fibric acid derivatives (such as gemfibrozil, bezafibrate, or fenofibrate)
- the antibiotics erythromycin, clarithromycin, and telithromycin
- HIV protease inhibitors (such as indinavir, nelfinavir, ritonavir, and saquinavir)
- the antidepressant nefazodone
- amiodarone (a drug used to treat an irregular heartbeat)
- verapamil or diltiazem (a drug used to treat high blood pressure, chest pain associated with heart disease, or other heart conditions)
- large quantities of grapefruit juice (>1 quart daily)
- large doses (≥1 g/day) of niacin or nicotinic acid

Tell your doctor if you are taking niacin or a niacin-containing product, as this may increase your risk of muscle problems, especially if you are Chinese.

It is also important to tell your doctor if you are taking coumarin anticoagulants (drugs that prevent blood clots, such as warfarin).

Tell your doctor about any prescription and nonprescription medicines you are taking or plan to take, including natural or herbal remedies.

Tell your doctor about all your medical conditions including allergies.

Tell your doctor if you:

- drink substantial quantities of alcohol or ever had liver problems. VYTORIN may not be right for you.
- are pregnant or plan to become pregnant. Do not use VYTORIN if you are pregnant, trying to become pregnant or suspect that you are pregnant. If you become pregnant while taking VYTORIN, stop taking it and contact your doctor immediately.
- are breast-feeding. Do not use VYTORIN if you are breast-feeding.

Tell other doctors prescribing a new medication that you are taking VYTORIN.

How should I take VYTORIN?

Your doctor has prescribed your dose of VYTORIN. The available doses of VYTORIN are 10/10, 10/20, 10/40, and 10/80. The usual daily starting dose is VYTORIN 10/20.

- Take VYTORIN once a day, in the evening, with or without food.
- Try to take VYTORIN as prescribed. If you miss a dose, do not take an extra dose. Just resume your usual schedule.
- Continue to follow a cholesterol-lowering diet while taking VYTORIN. Ask your doctor if you need diet information.
- Keep taking VYTORIN unless your doctor tells you to stop. If you stop taking VYTORIN, your cholesterol may rise again.

What should I do in case of an overdose?

Contact your doctor immediately.

What are the possible side effects of VYTORIN?

See your doctor regularly to check your cholesterol level and to check for side effects. Your doctor may do blood tests to check your liver before you start taking VYTORIN and during treatment.

In clinical studies patients reported the following common side effects while taking VYTORIN: headache, muscle pain, and diarrhea (see What should I tell my doctor before and while taking VYTORIN?).

The following side effects have been reported in general use with VYTORIN or with ezetimibe or simvastatin tablets (tablets that contain the active ingredients of VYTORIN):

- allergic reactions including swelling of the face, lips, tongue, and/or throat that may cause difficulty in breathing or swallowing (which may require treatment right away), rash, hives; raised red rash, sometimes with target-shaped lesions; joint pain; muscle pain; alterations in some laboratory blood tests; liver problems (sometimes serious); inflammation of the pancreas; nausea; dizziness; tingling sensation; depression; gallstones; inflammation of the gallbladder; trouble sleeping; poor memory; erectile dysfunction; breathing problems including persistent cough and/or shortness of breath or fever.

Tell your doctor if you are having these or any other medical problems while on VYTORIN. This is not a complete list of side effects. For a complete list, ask your doctor or pharmacist.

What should I know about high cholesterol?

Cholesterol is a type of fat found in your blood. Cholesterol comes from two sources. It is produced by your body and it comes from the food you eat. Your total cholesterol is made up of both LDL and HDL cholesterol.

LDL cholesterol is called “bad” cholesterol because it can build up in the wall of your arteries and form plaque. Over time, plaque build-up can cause a narrowing of the arteries. This narrowing can slow or block blood flow to your heart, brain, and other organs. High LDL cholesterol is a major cause of heart disease and one of the causes for stroke.

HDL cholesterol is called “good” cholesterol because it keeps the bad cholesterol from building up in the arteries.

Triglycerides also are fats found in your body.

General Information about VYTORIN

Medicines are sometimes prescribed for conditions that are not mentioned in patient information leaflets. Do not use VYTORIN for a condition for which it was not prescribed. Do not give VYTORIN to other people, even if they have the same condition you have. It may harm them.

This summarizes the most important information about VYTORIN. If you would like more information, talk with your doctor. You can ask your pharmacist or doctor for information about VYTORIN that is written for health professionals. For additional information, visit the following web site: vytorin.com.

Inactive ingredients:

Butylated hydroxyanisole NF, citric acid monohydrate USP, croscarmellose sodium NF, hypromellose USP, lactose monohydrate NF, magnesium stearate NF, microcrystalline cellulose NF, and propyl gallate NF.

Issued May 2010

9619517

Manufactured for:
Merck/Schering-Plough Pharmaceuticals
North Wales, PA 19454, USA

By:
MSD Technology Singapore Pte. Ltd.
Singapore 637766

Or

Merck Sharp & Dohme (Italia) S.p.A.
Via Emilia, 21
27100 – Pavia, Italy

Or

Merck Sharp & Dohme Ltd.
Cramlington, Northumberland, UK NE23 3JU

Or

Jointly manufactured by:
Merck Sharp & Dohme (Italia) S.p.A.
Via Emilia, 21
27100 – Pavia, Italy
and
MSD Technology Singapore Pte. Ltd.
Singapore 637766

U.S. Patent Nos. 5,846,966 and RE37,721

Repackaged by:

Rebel Distributors Corp

Thousand Oaks, CA 91320

This is a representative sample of the packaging. Please see How Supplied section for a complete list of available packaging.

PRINCIPAL DISPLAY PANEL - Bottle Label 10/20

VYTORIN® 10/20
(ezetimibe/simvastatin)

Each tablet contains 10 mg ezetimibe and 20 mg simvastatin.

Store at 20-25°C (68-77°F). [See USP Controlled Room Temperature.]
Keep container tightly closed.

Rx only

USUAL ADULT DOSAGE: See accompanying circular.

30 Tablets

NDC 21695-325-30

Dist. by:
MERCK/Schering-Plough Pharmaceuticals
North Wales, PA 19454, U. S. A.

Jointly manuf. by:
Merck Sharp & Dohme (Italia) S.p.A.
Via Emilia, 21
27100 - Pavia, Italy
and
MSD Technology Singapore Pte. Ltd.
Singapore 637766

Product of Singapore.

9732402
30 | No. 3874

Repackaged by:

Rebel Distributors Corp

Thousand Oaks, CA 91320

PRINCIPAL DISPLAY PANEL - Bottle Label 10/40

VYTORIN® 10/40
(ezetimibe/simvastatin)

Each tablet contains 10 mg ezetimibe and 40 mg simvastatin.

Store at 20-25°C (68-77°F). [See USP Controlled Room Temperature.]
Keep container tightly closed.

30 Tablets

NDC 21695-339-30

Rx only

USUAL ADULT DOSAGE: See accompanying circular.

Dist. by:
MERCK/Schering-Plough Pharmaceuticals
North Wales, PA 19454, U. S. A.

Manuf. by:
Merck Sharp & Dohme (Italia) S.p.A.
Via Emilia, 21
27100 - Pavia, Italy

Formulated in Italy.

9861900
30 | No. 3875

Repackaged by:

Rebel Distributors Corp

Thousand Oaks, CA 91320

PRINCIPAL DISPLAY PANEL - Bottle Label 10/80

VYTORIN® 10/80
(ezetimibe/simvastatin)

Each tablet contains 10 mg ezetimibe and 80 mg simvastatin.

Store at 20-25°C (68-77°F). [See USP Controlled Room Temperature.]
Keep container tightly closed.

30 Tablets

NDC 21695-827-30

Rx only

USUAL ADULT DOSAGE: See accompanying circular.

Dist. by:
MERCK/Schering-Plough Pharmaceuticals
North Wales, PA 19454, U. S. A.

Manuf. by:
MSD Technology Singapore Pte. Ltd.
Singapore 637766

Product of Singapore.

9732601
30 | No. 3876

Repackaged by:

Rebel Distributors Corp

Thousand Oaks, CA 91320